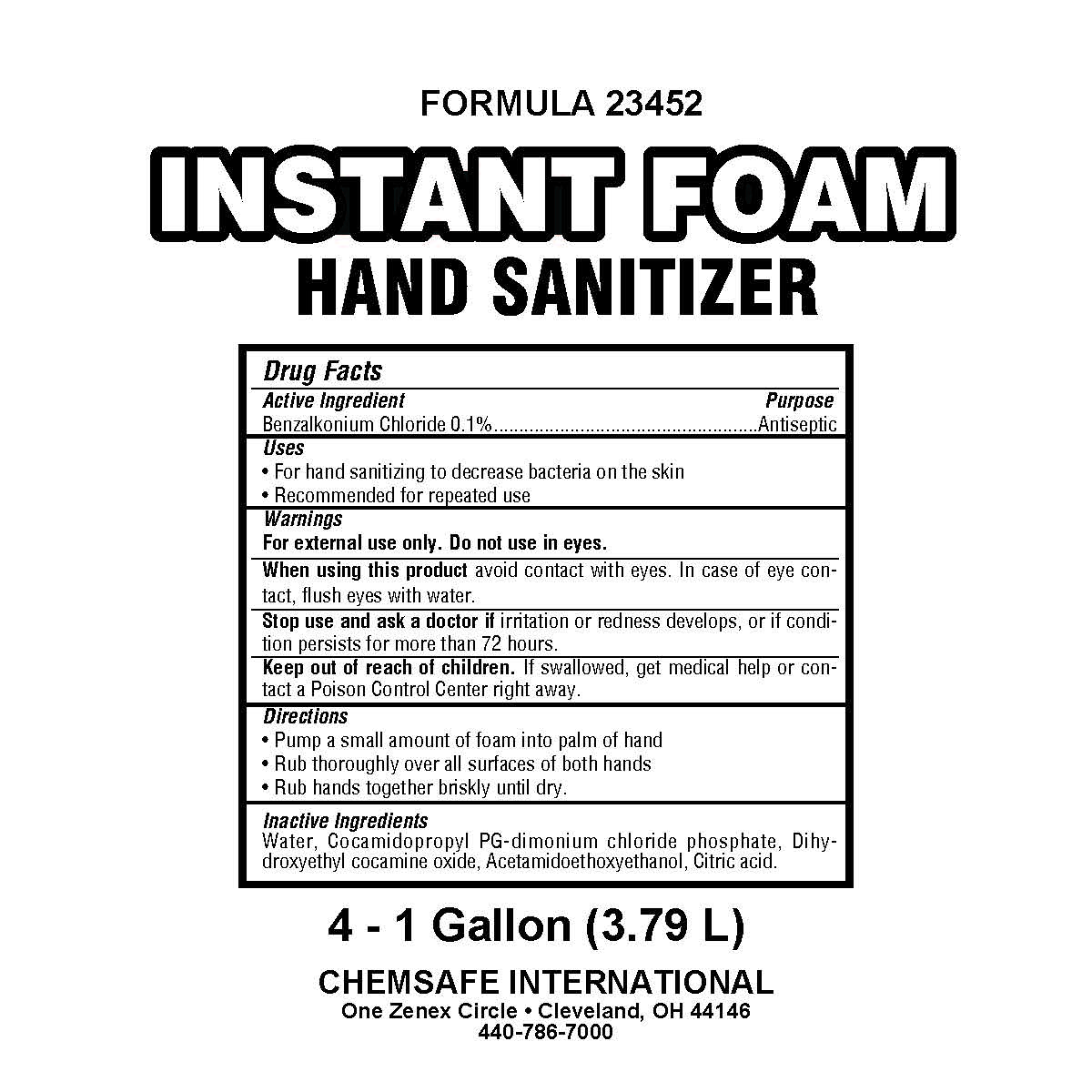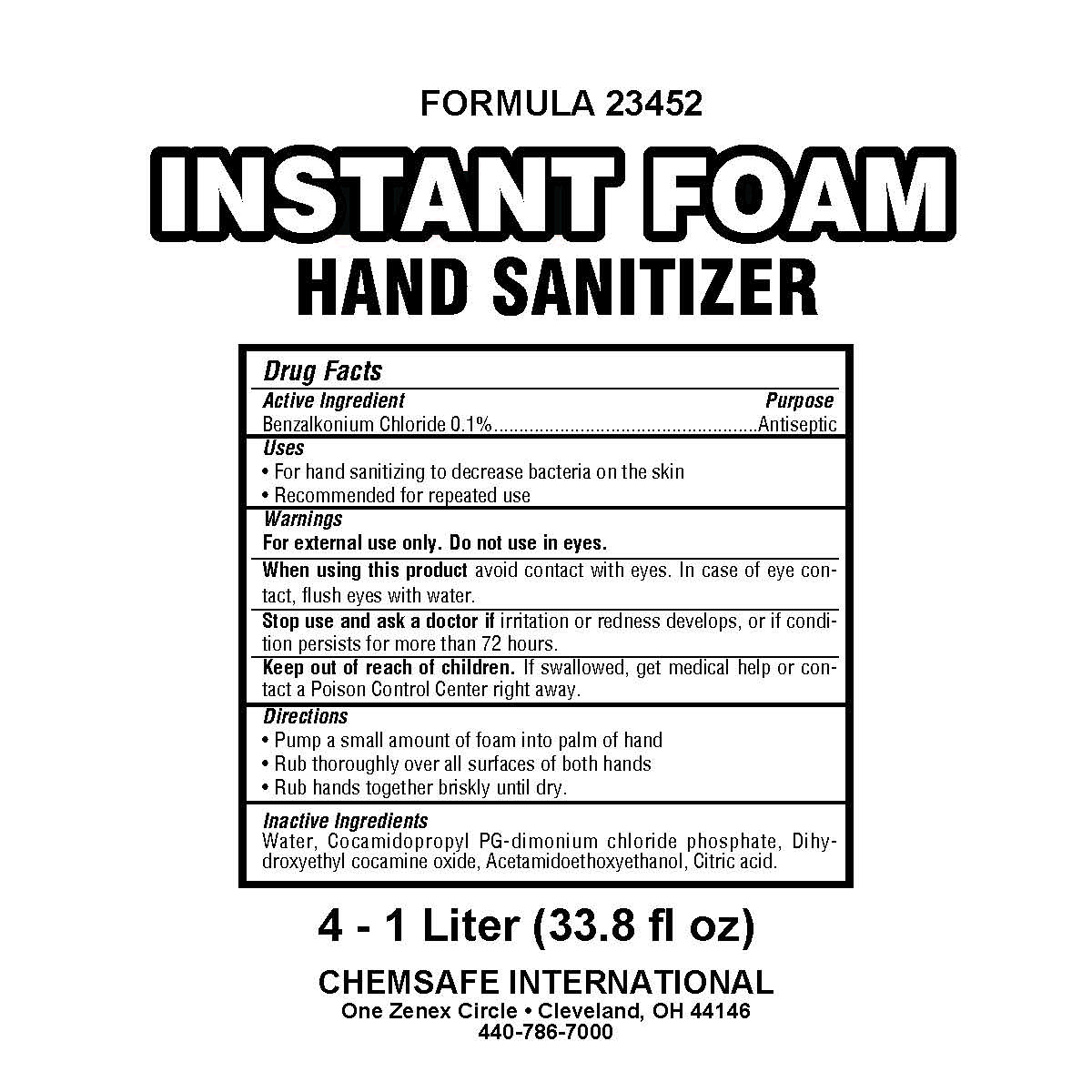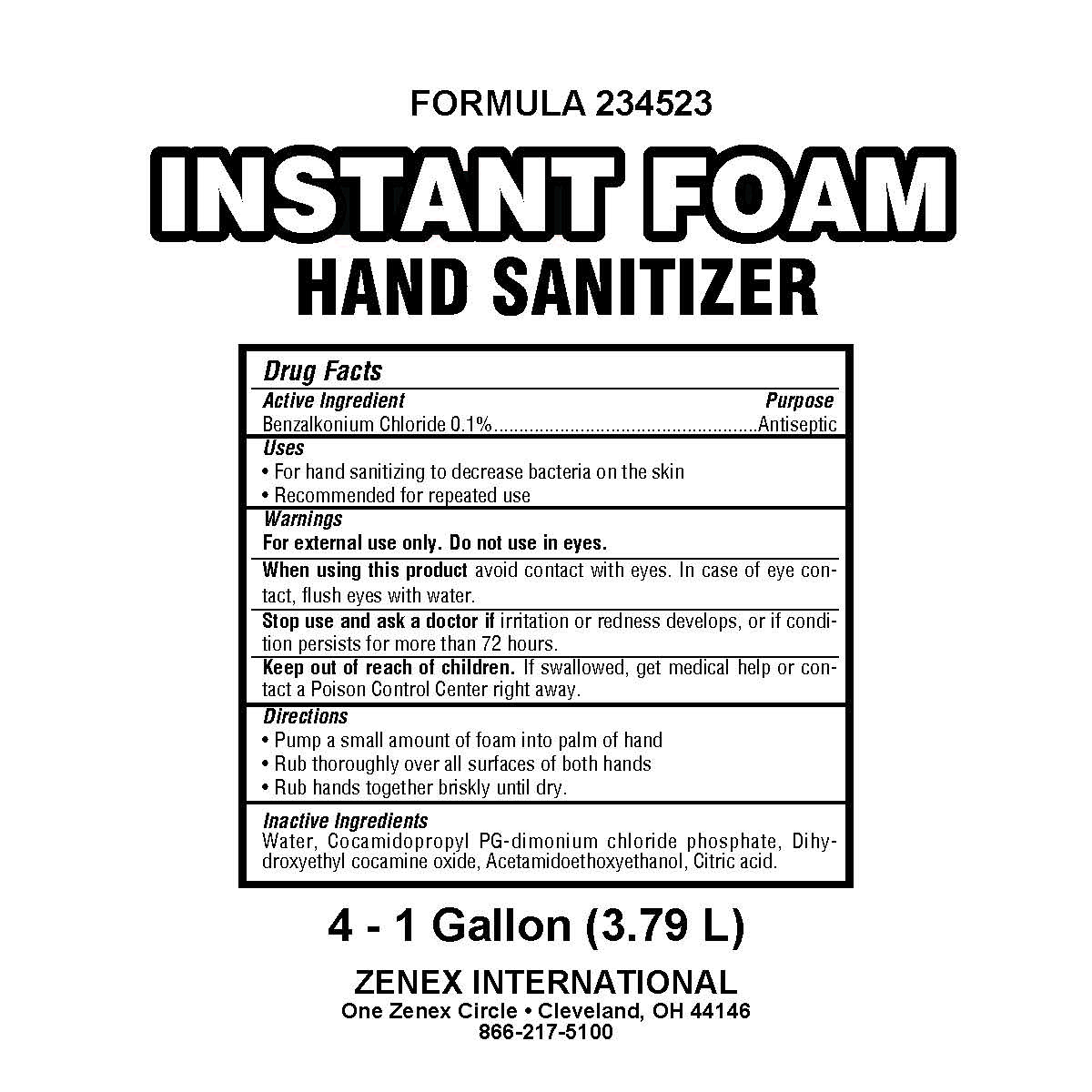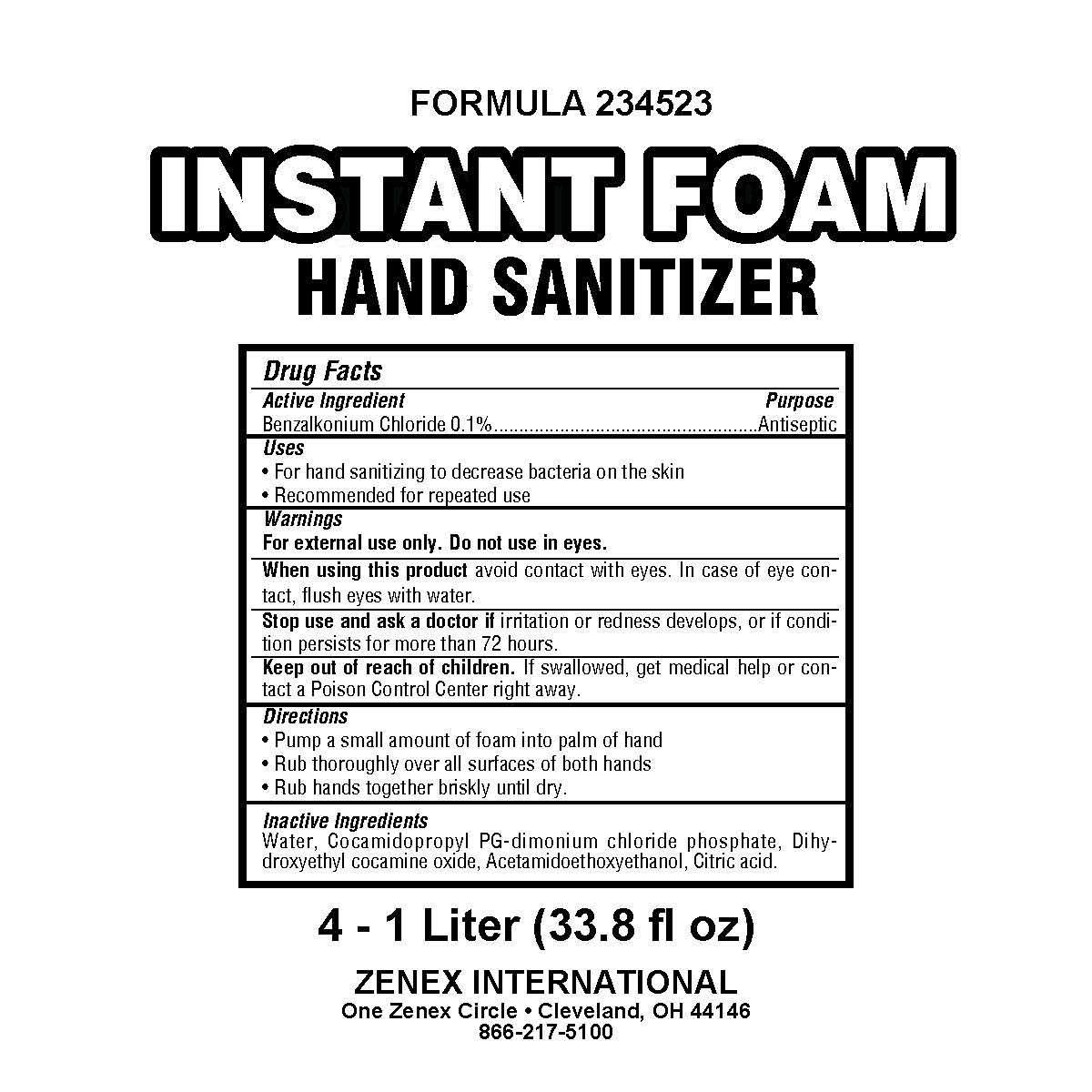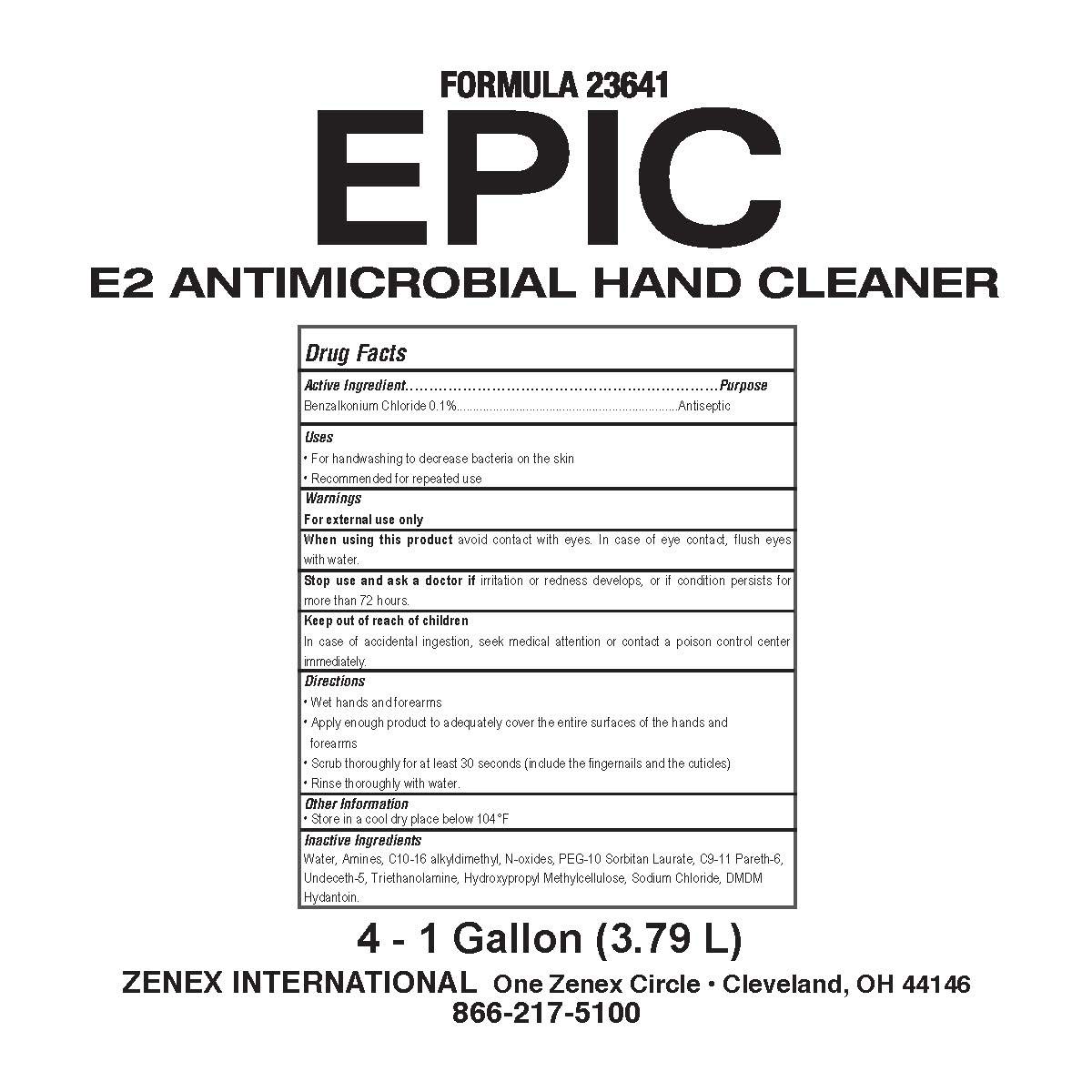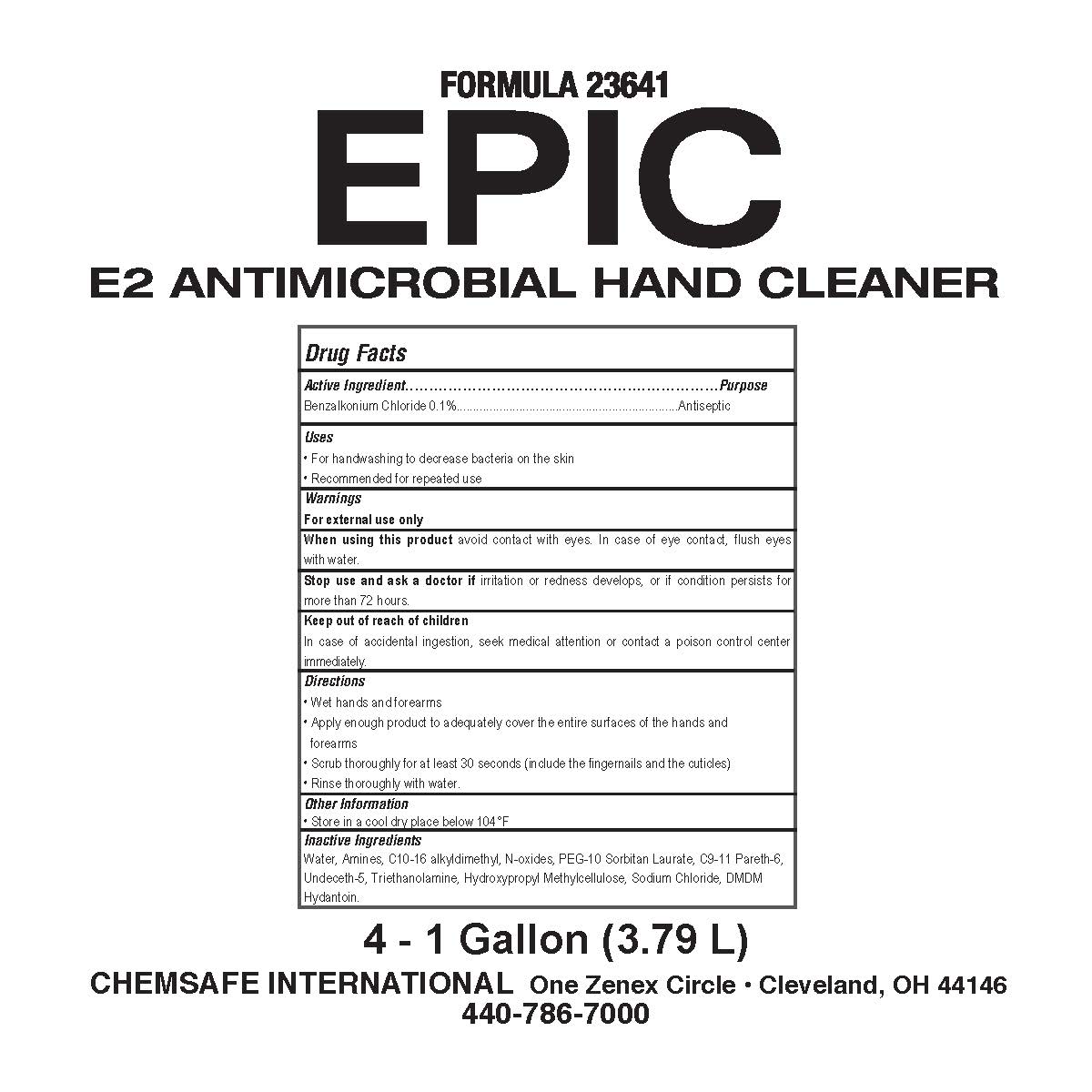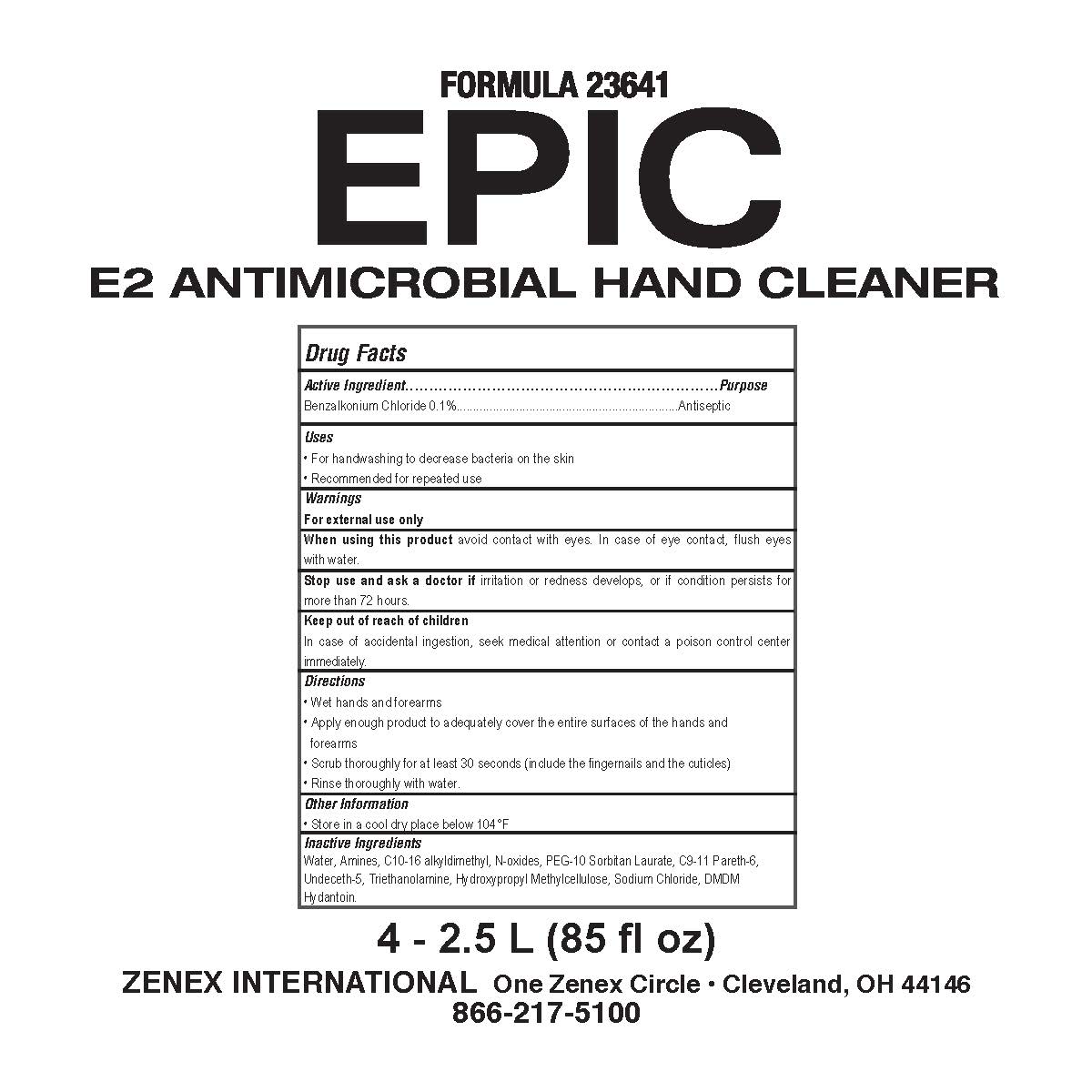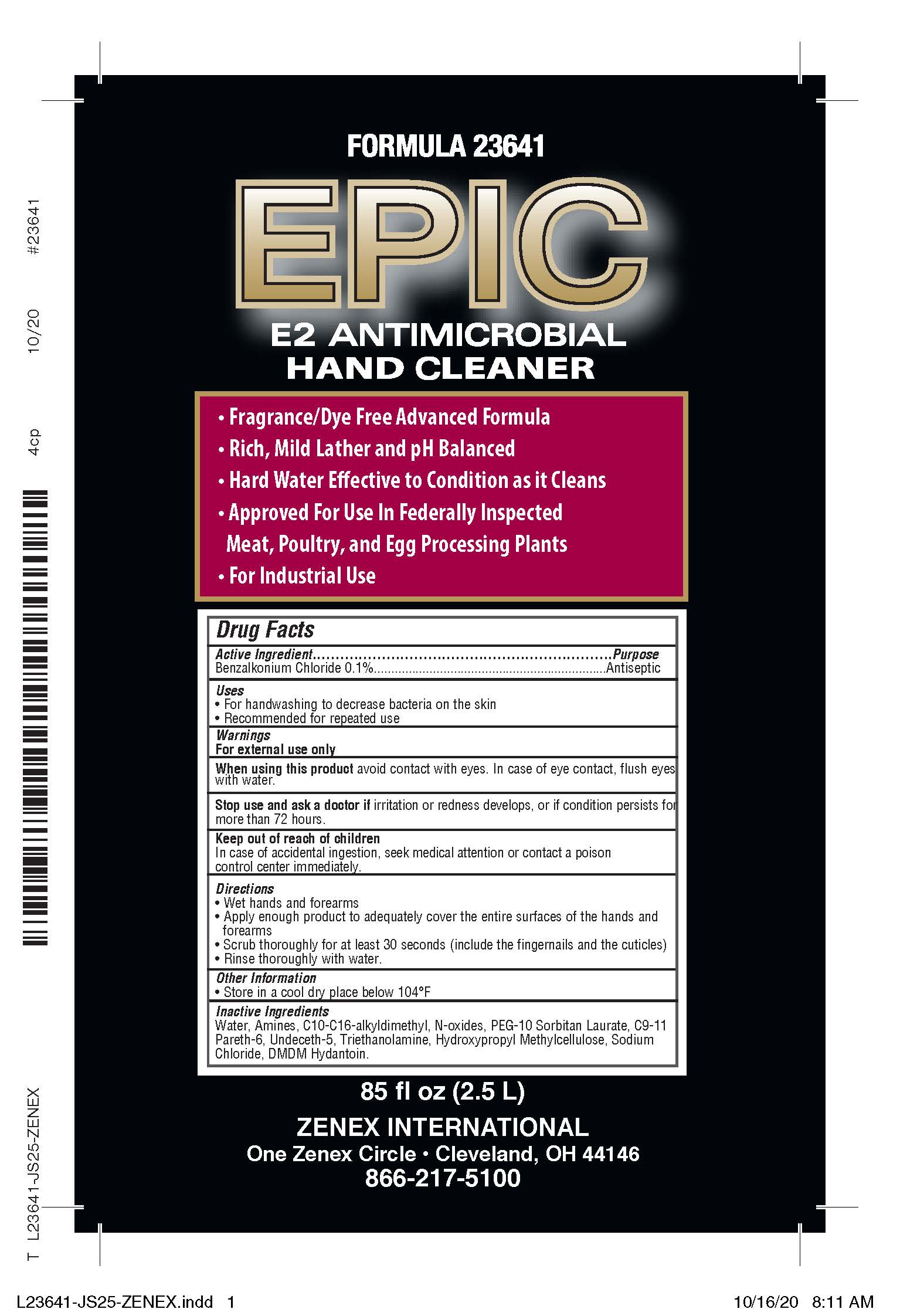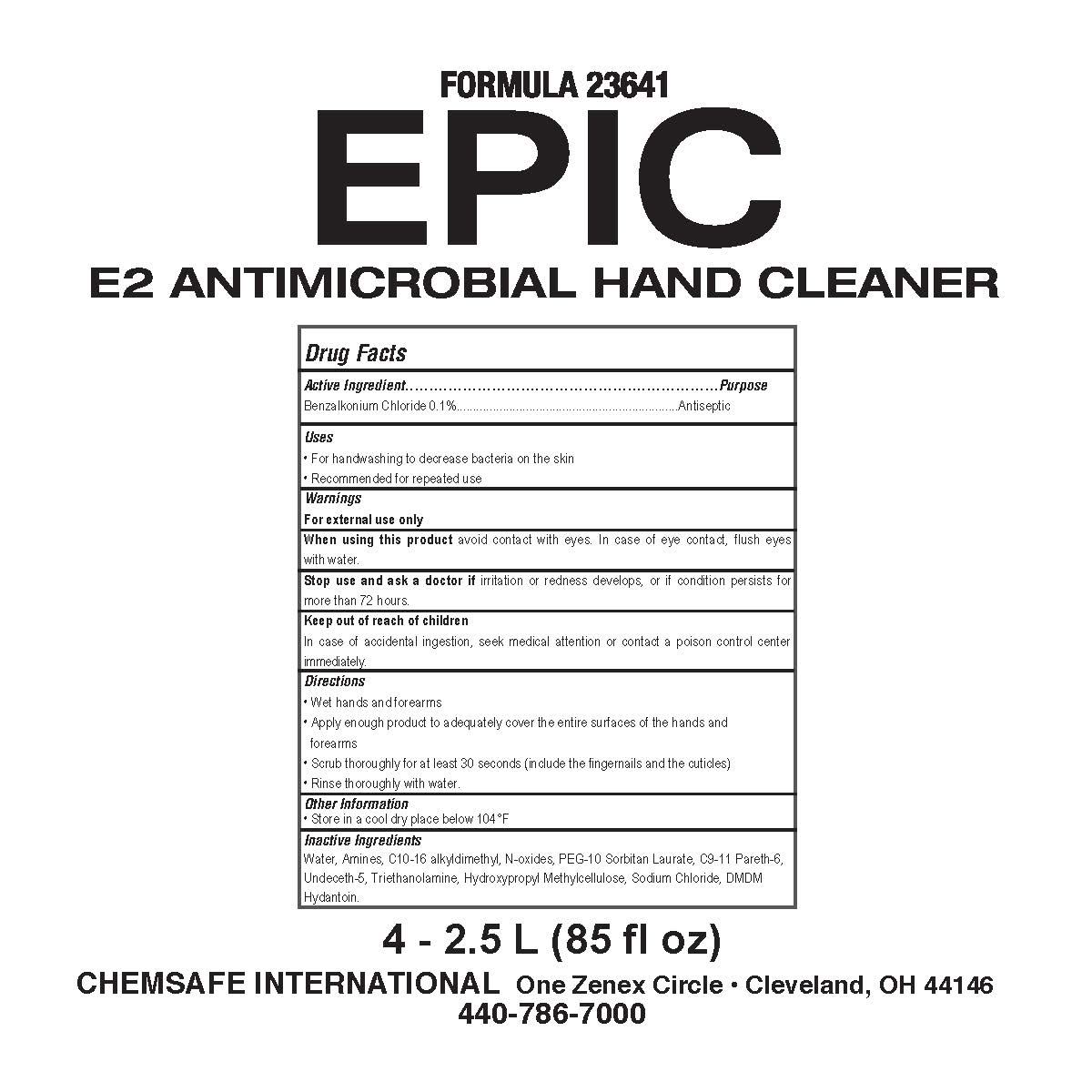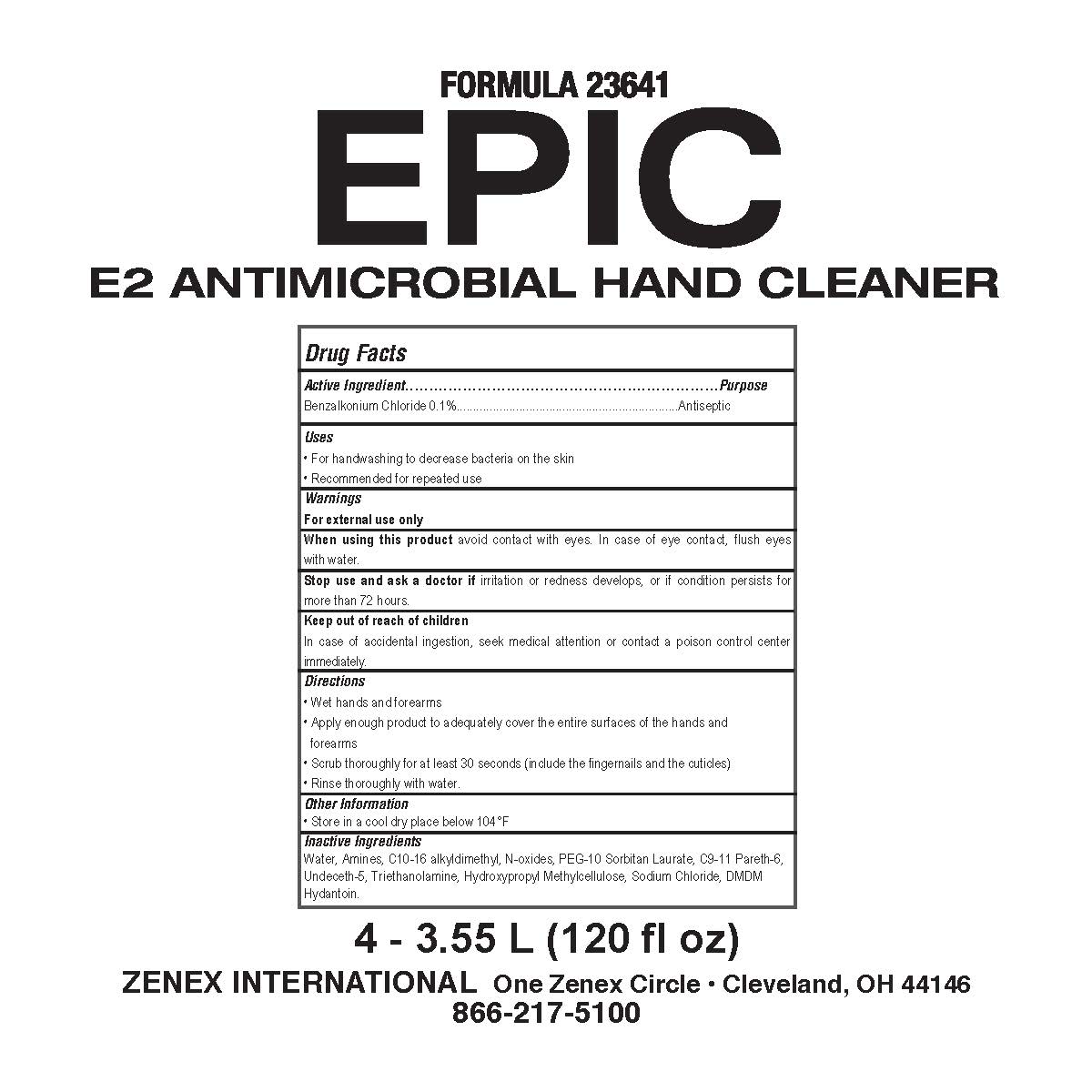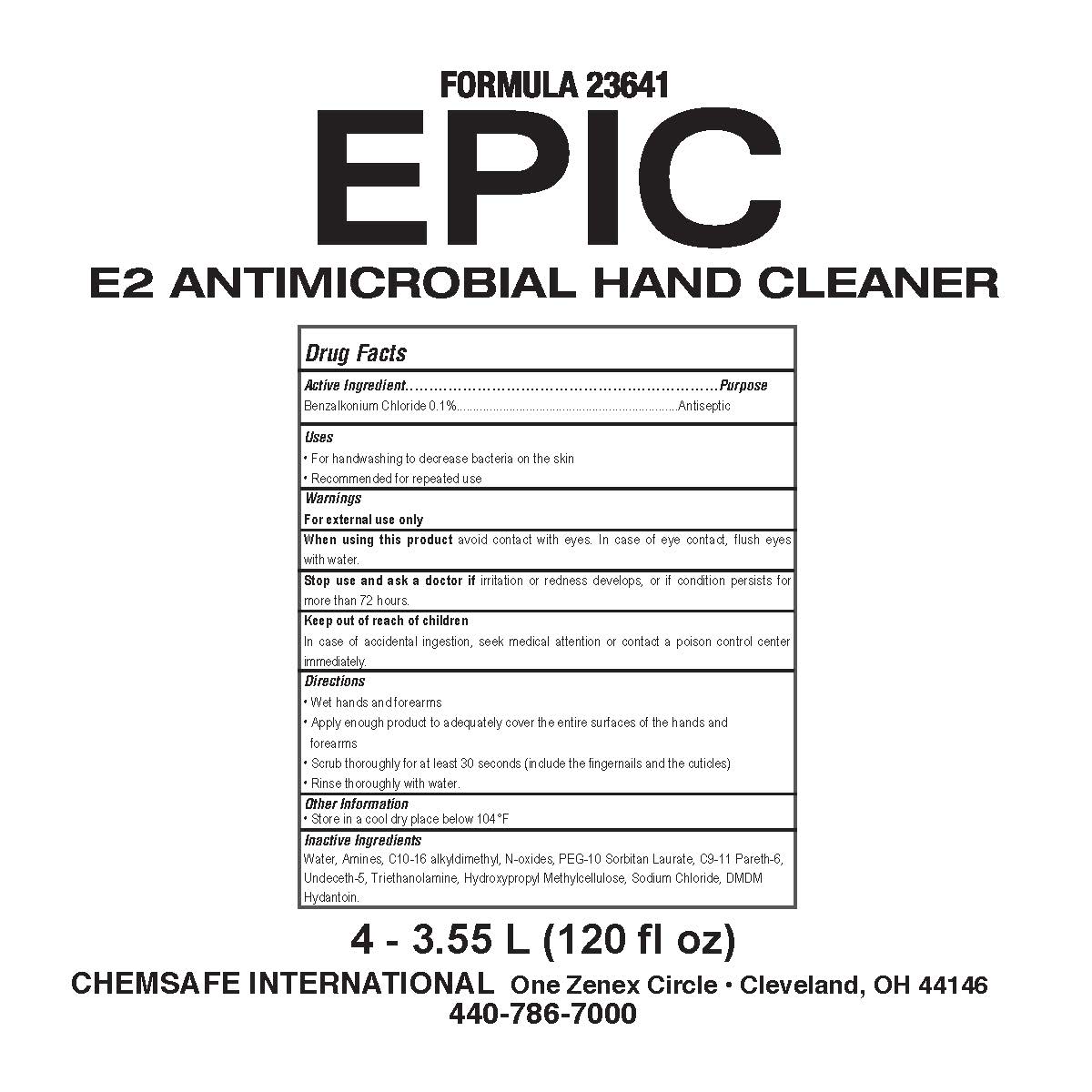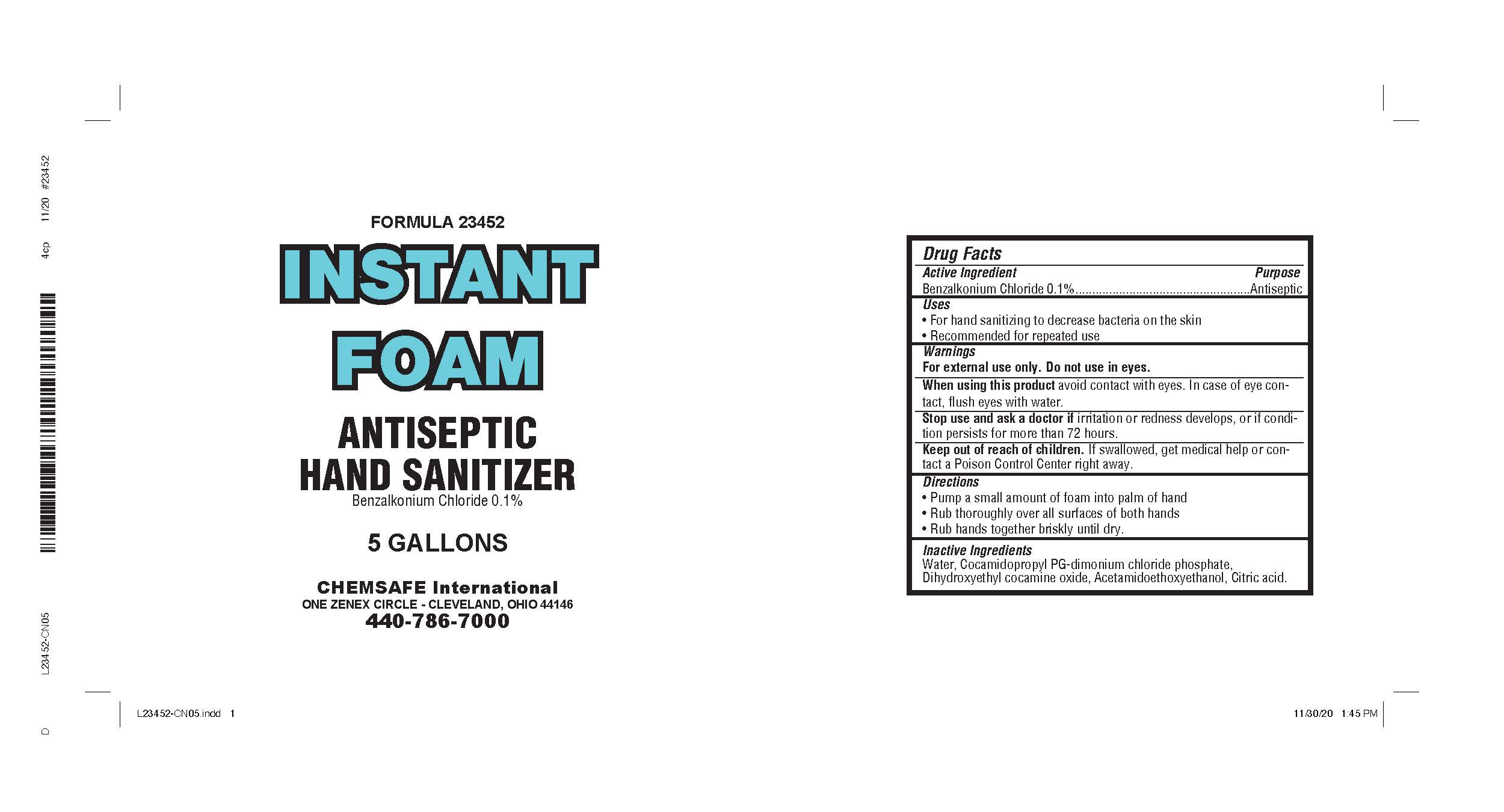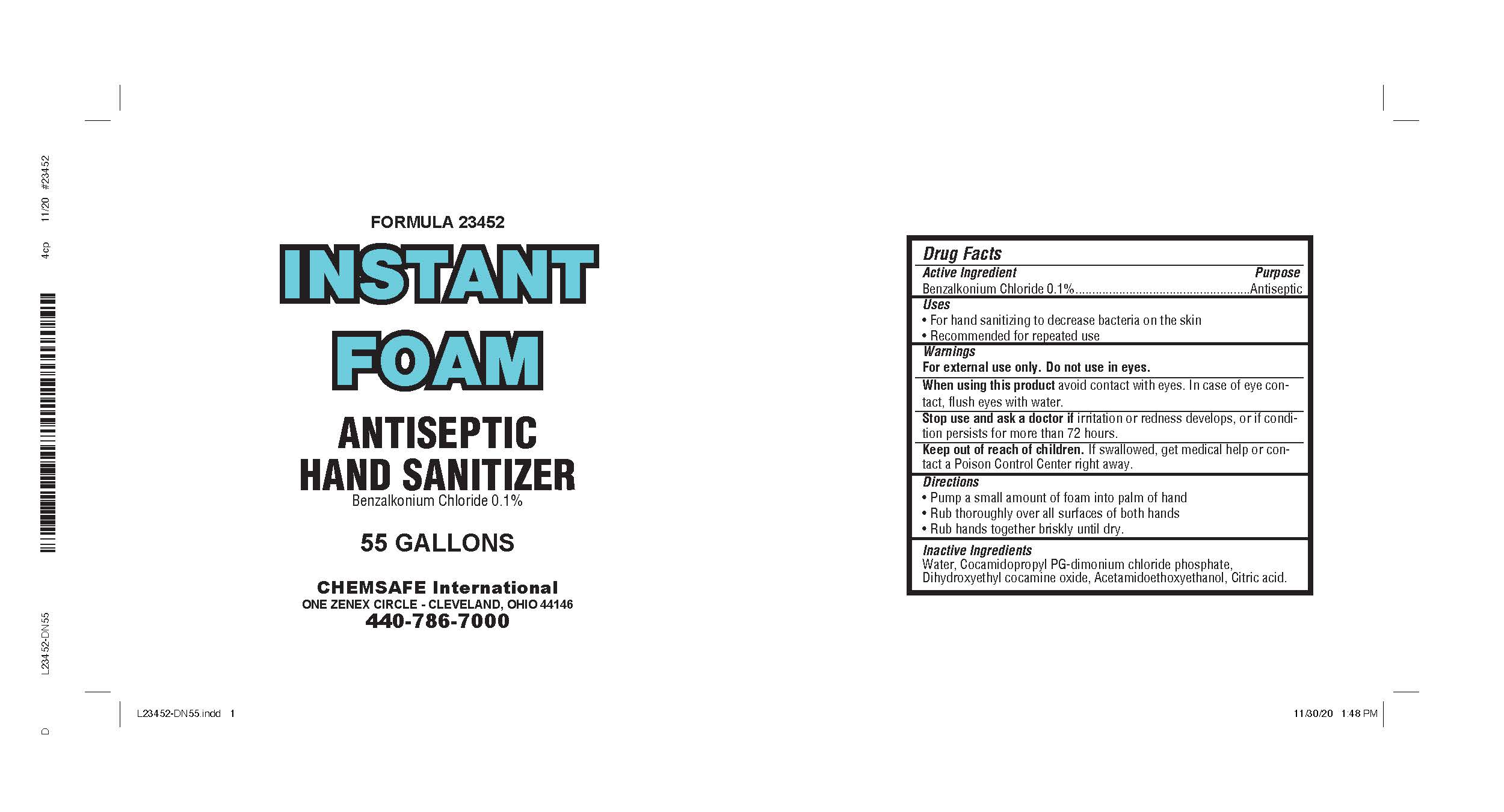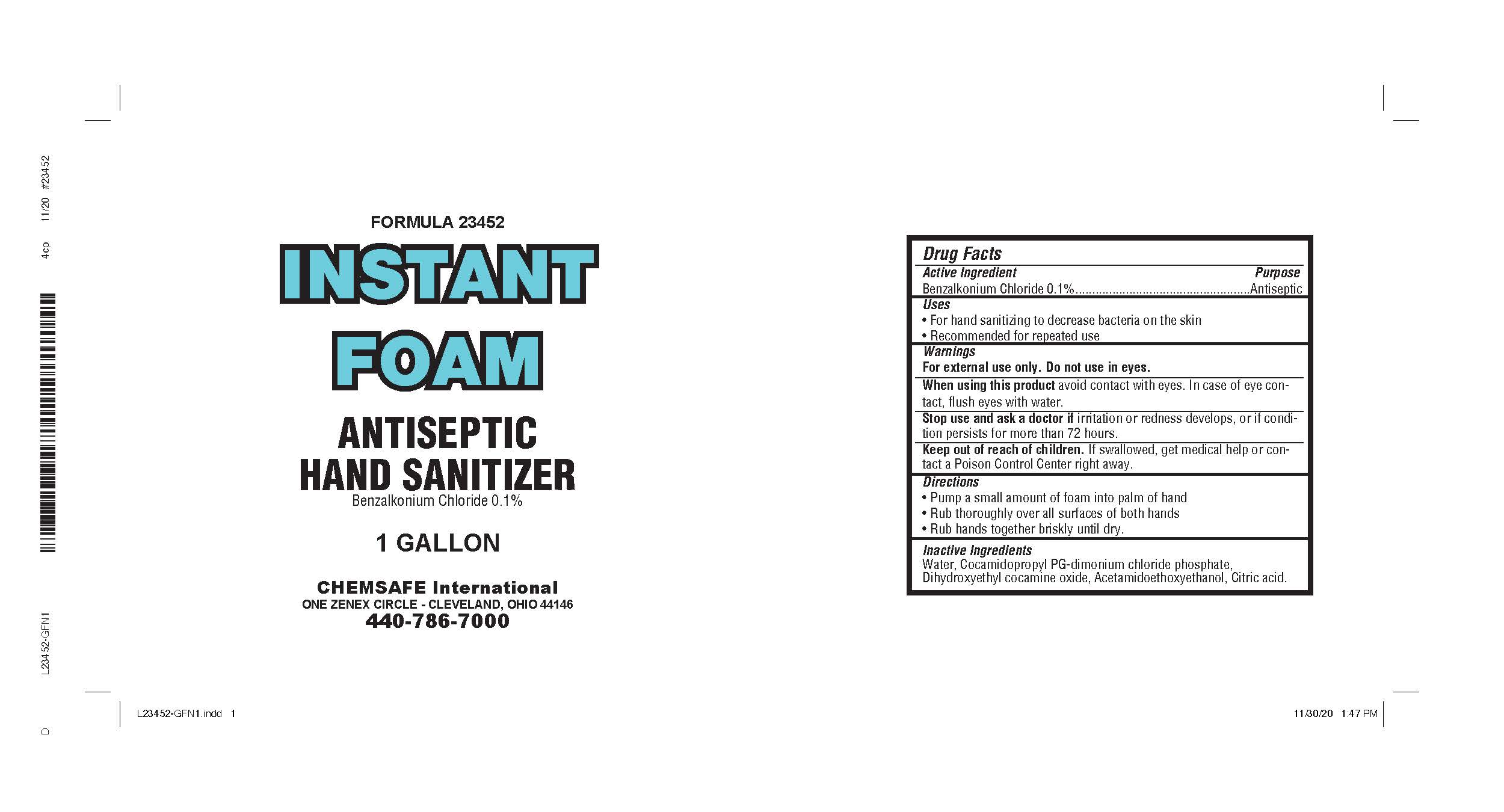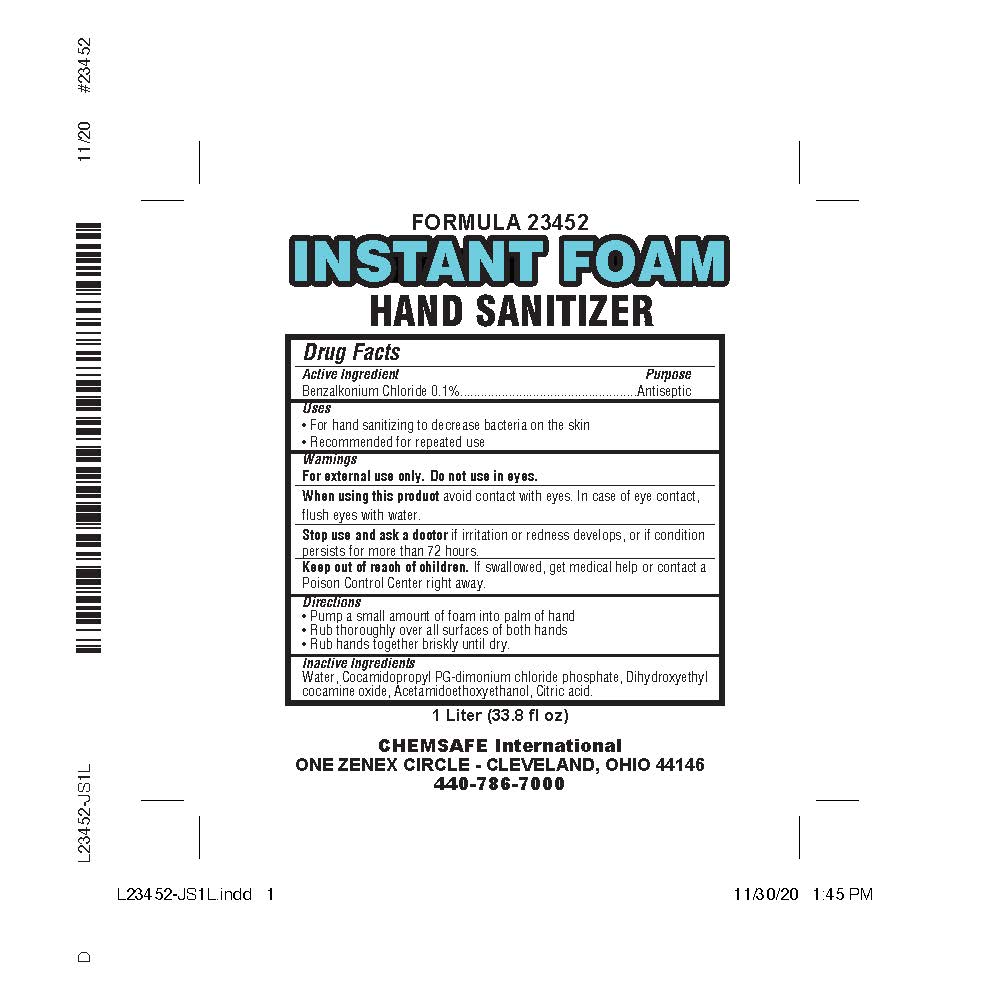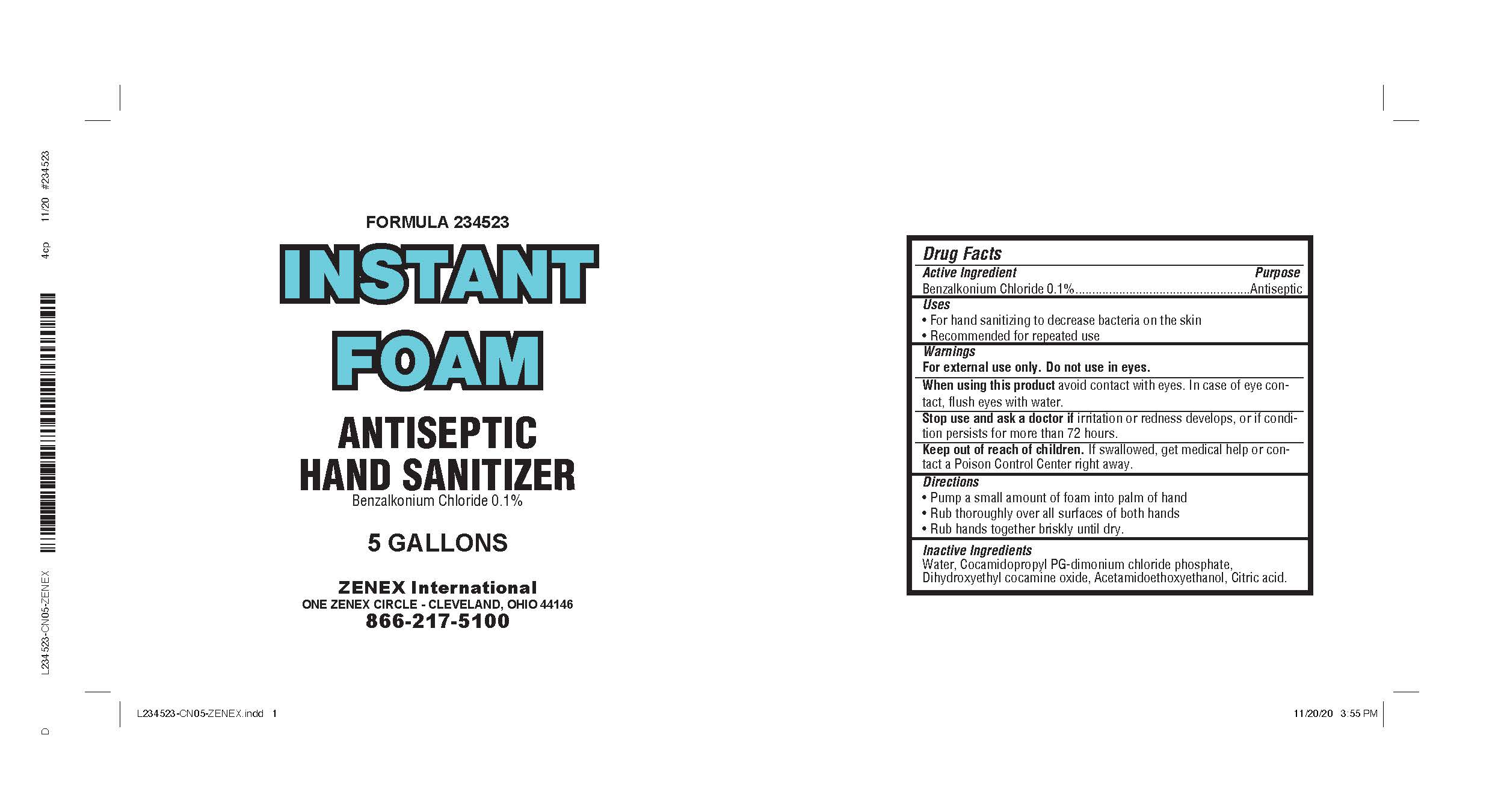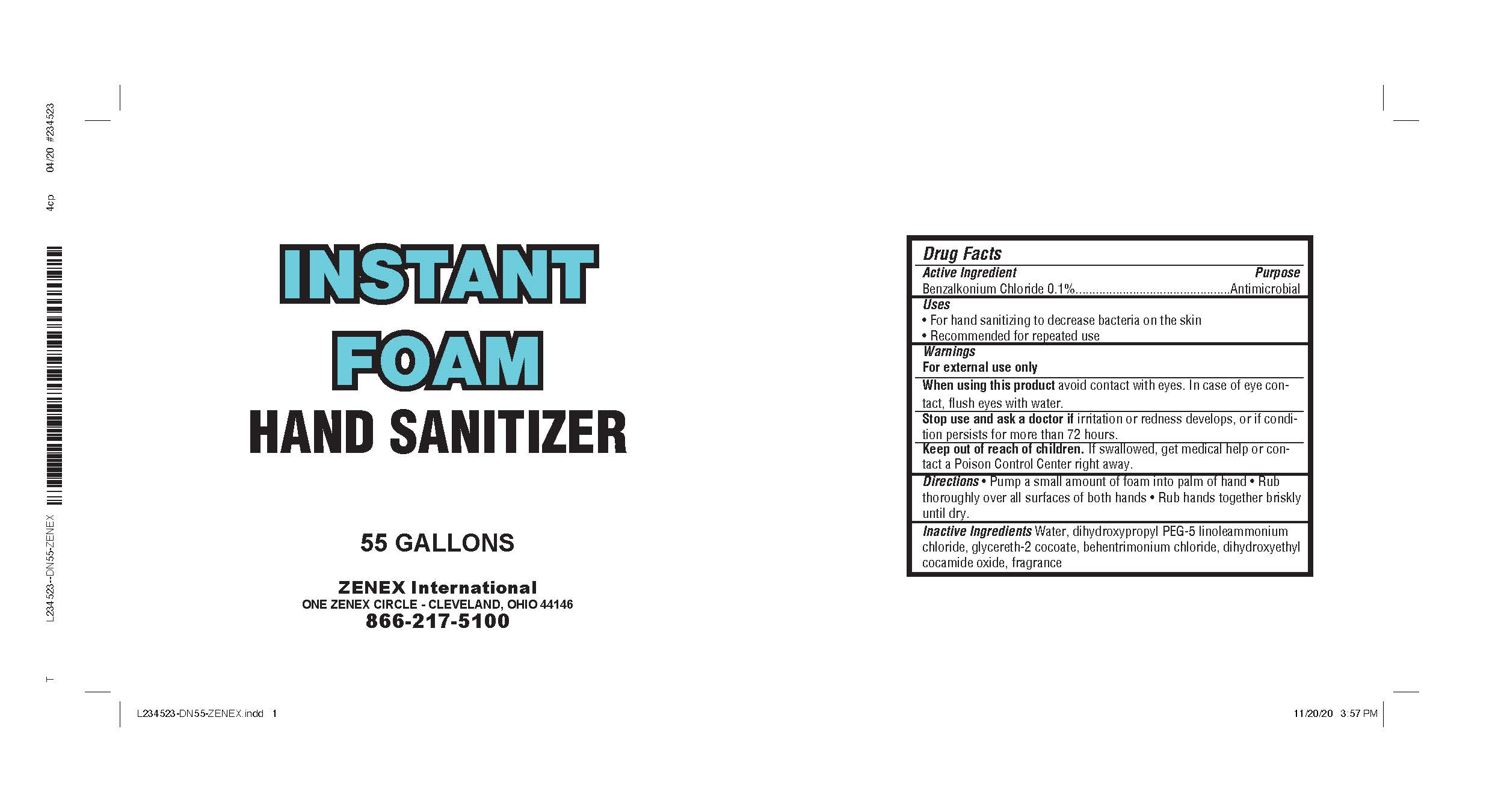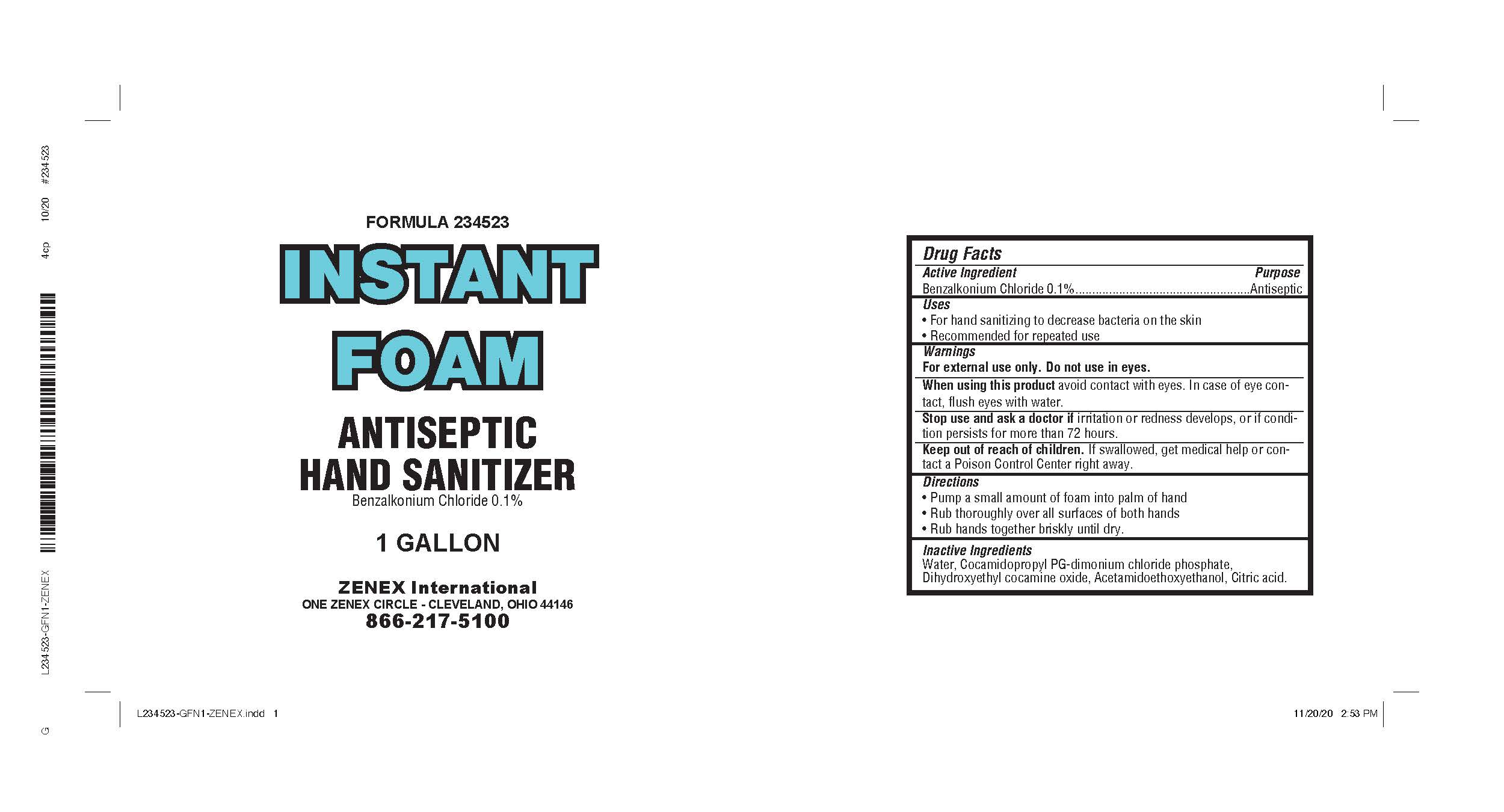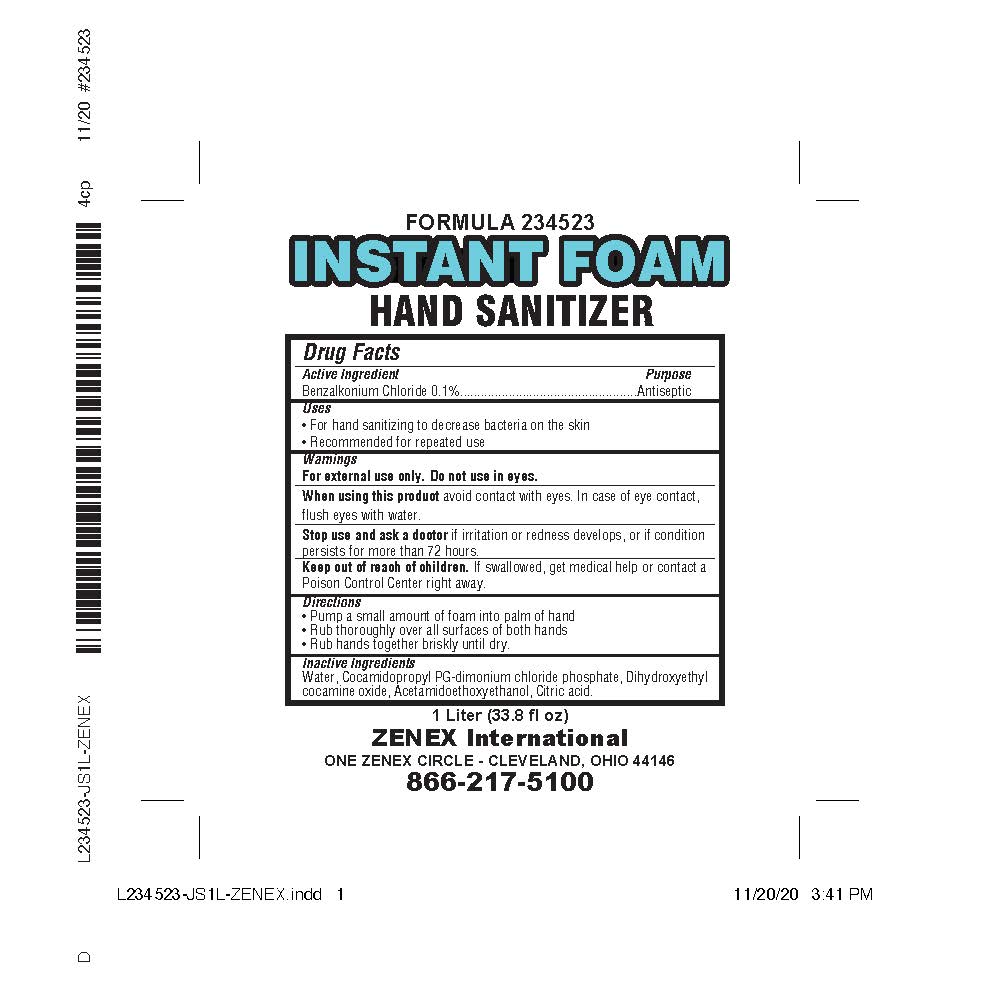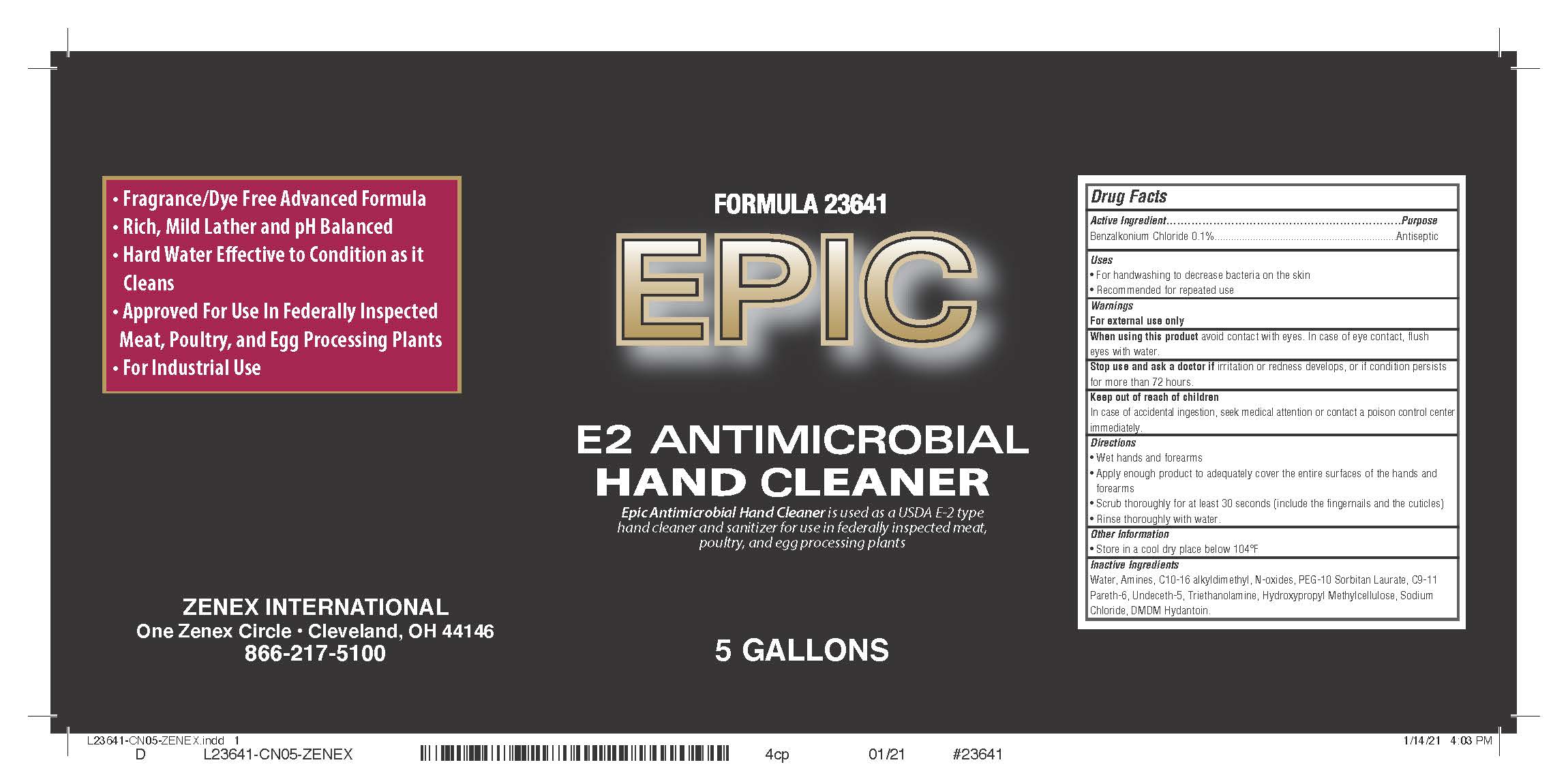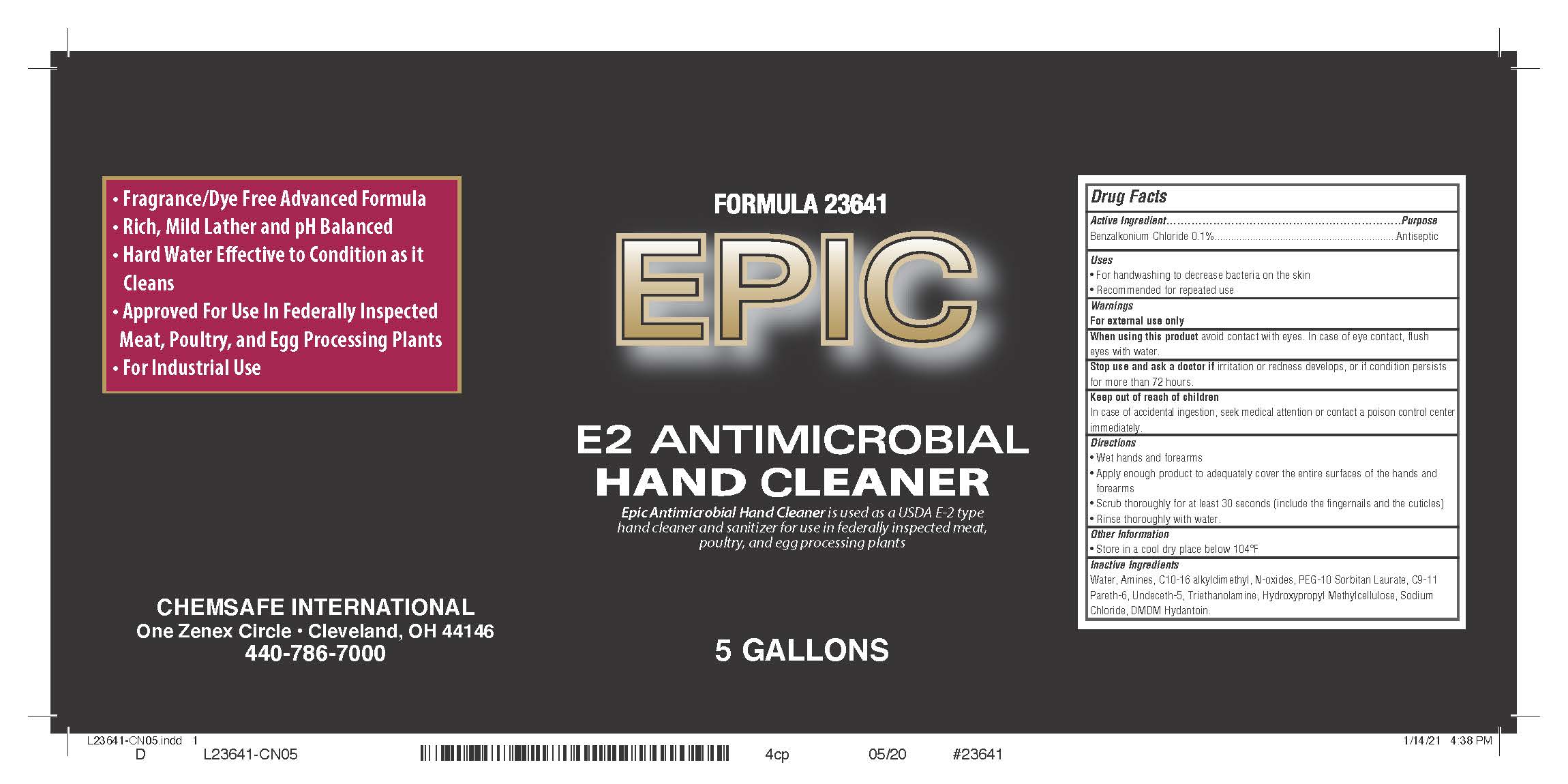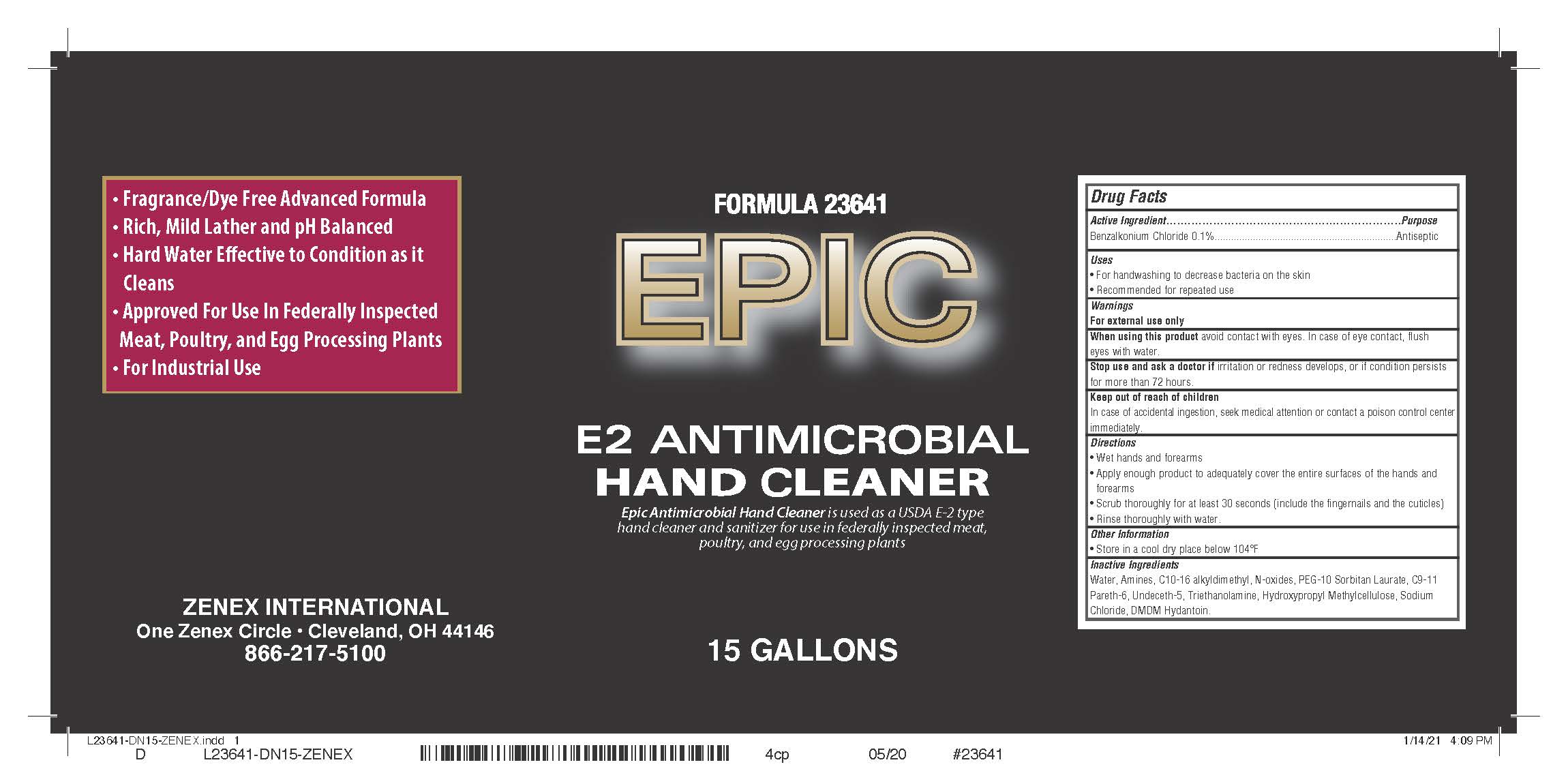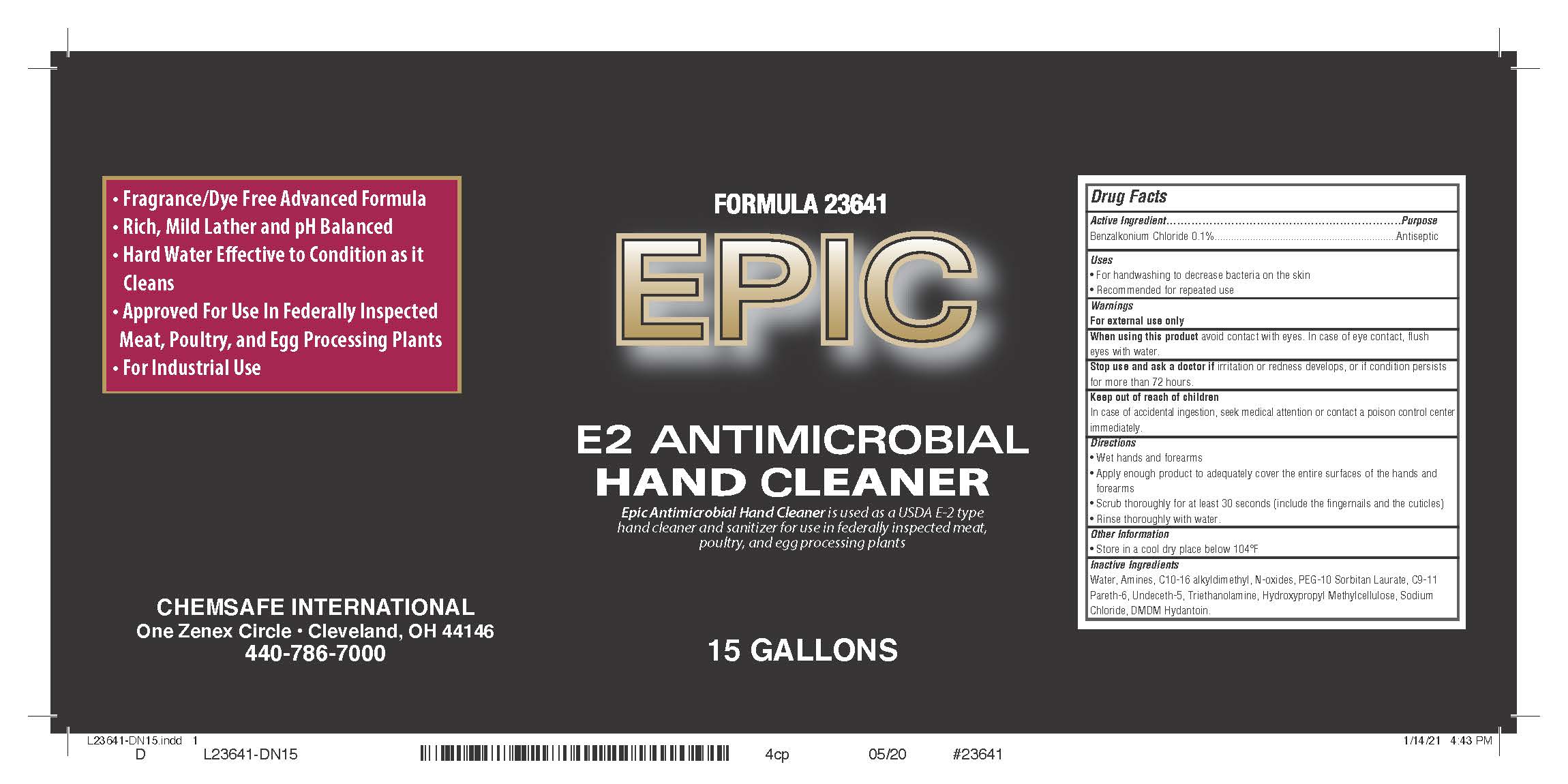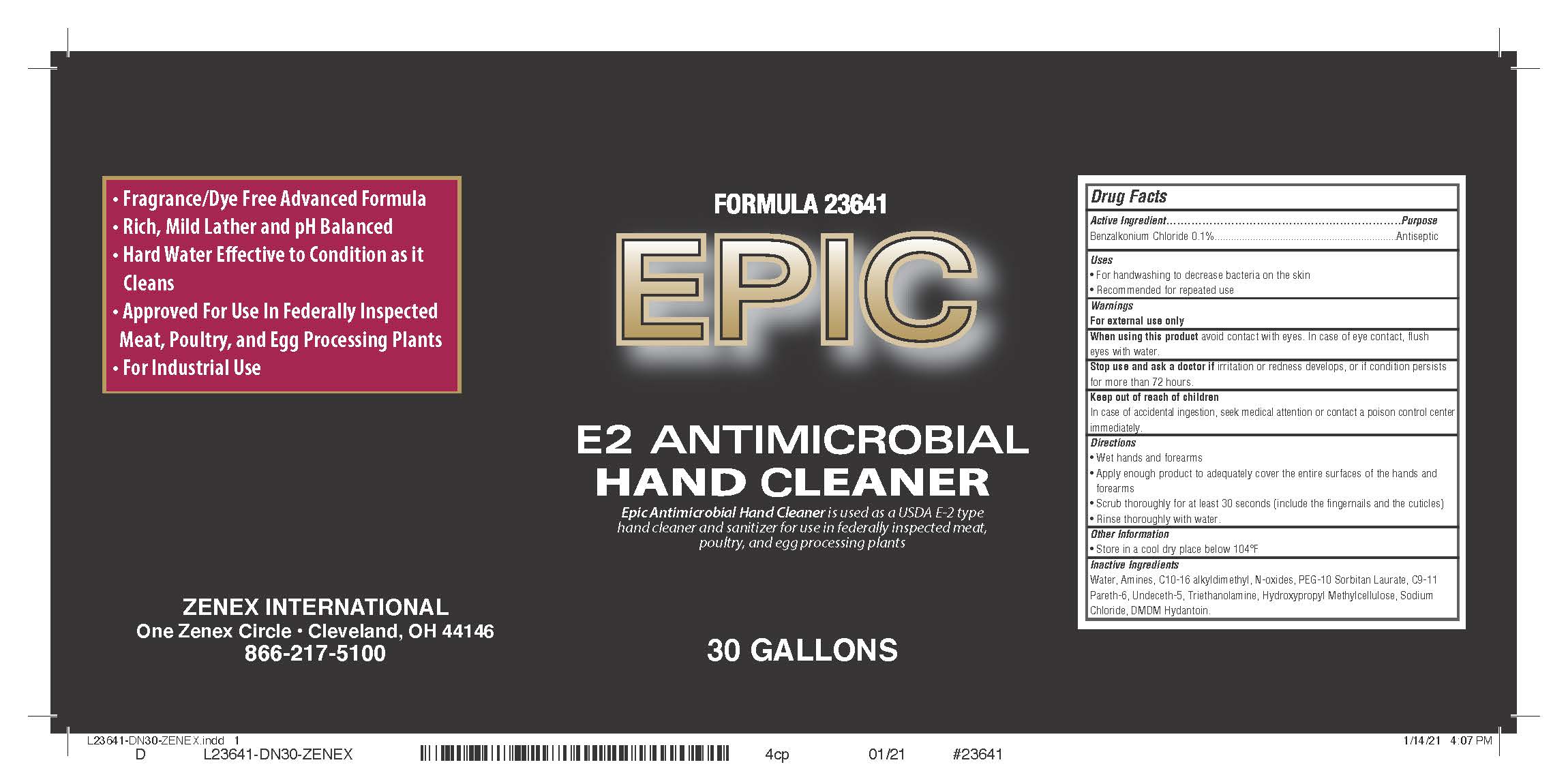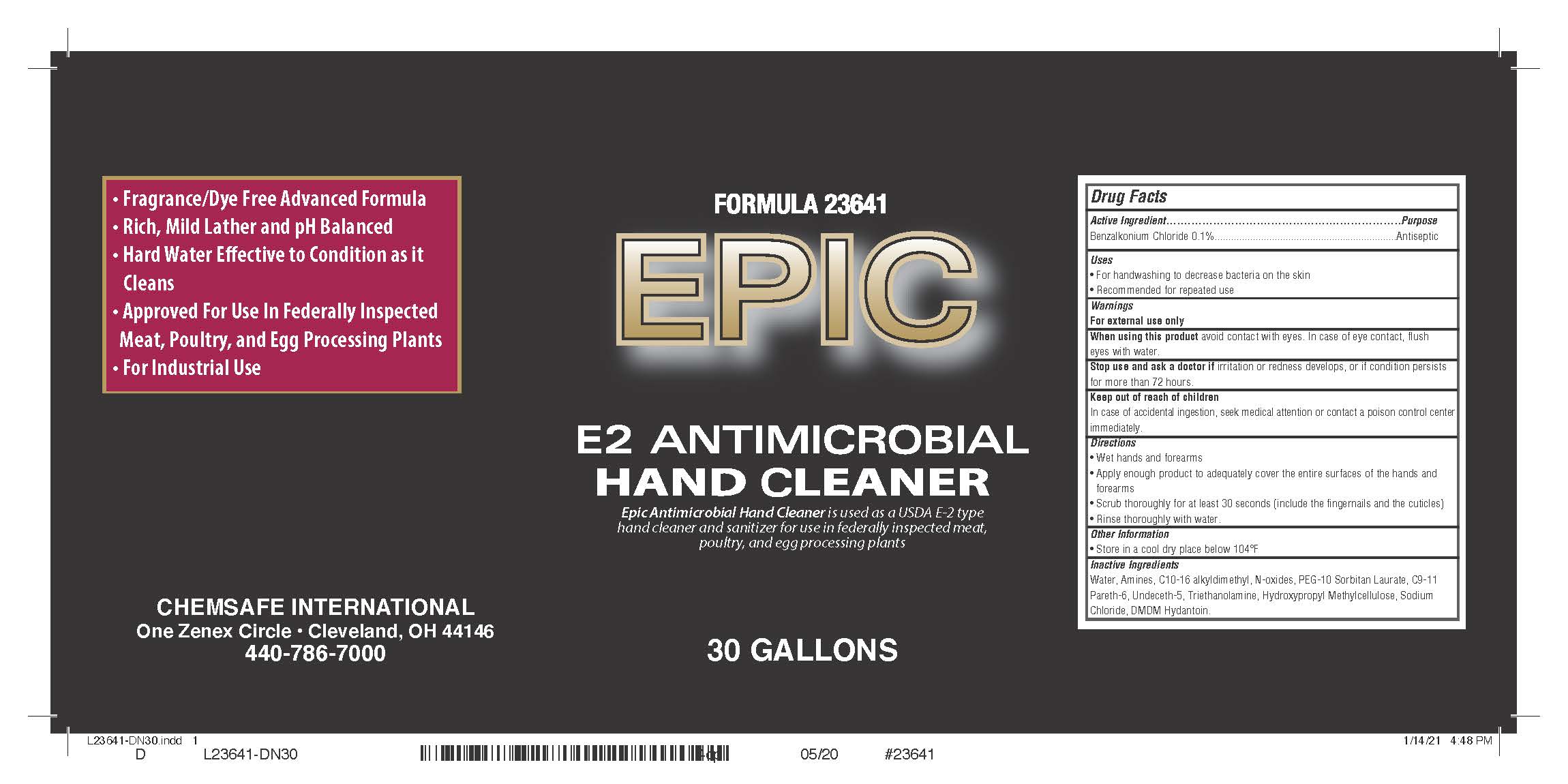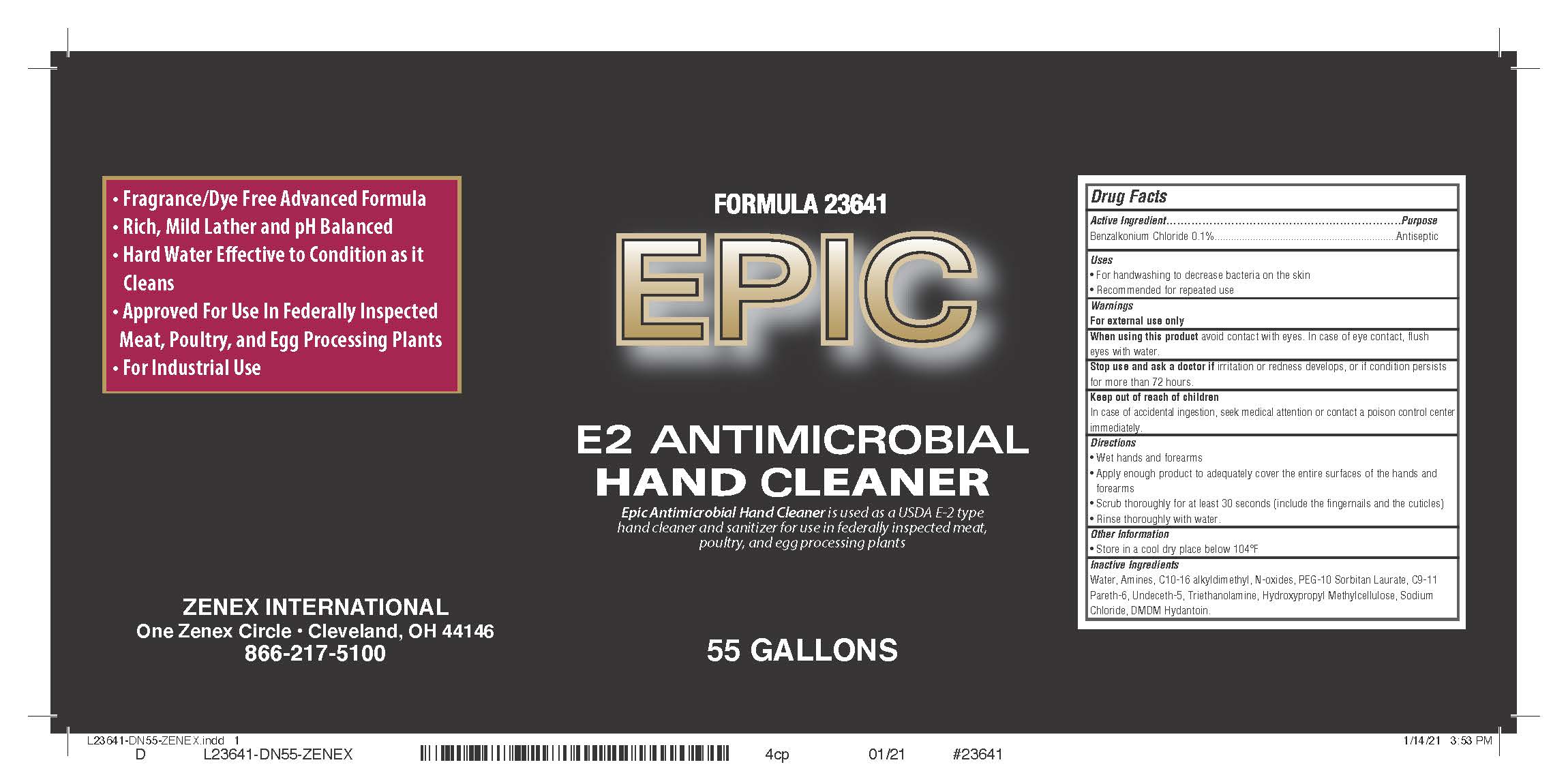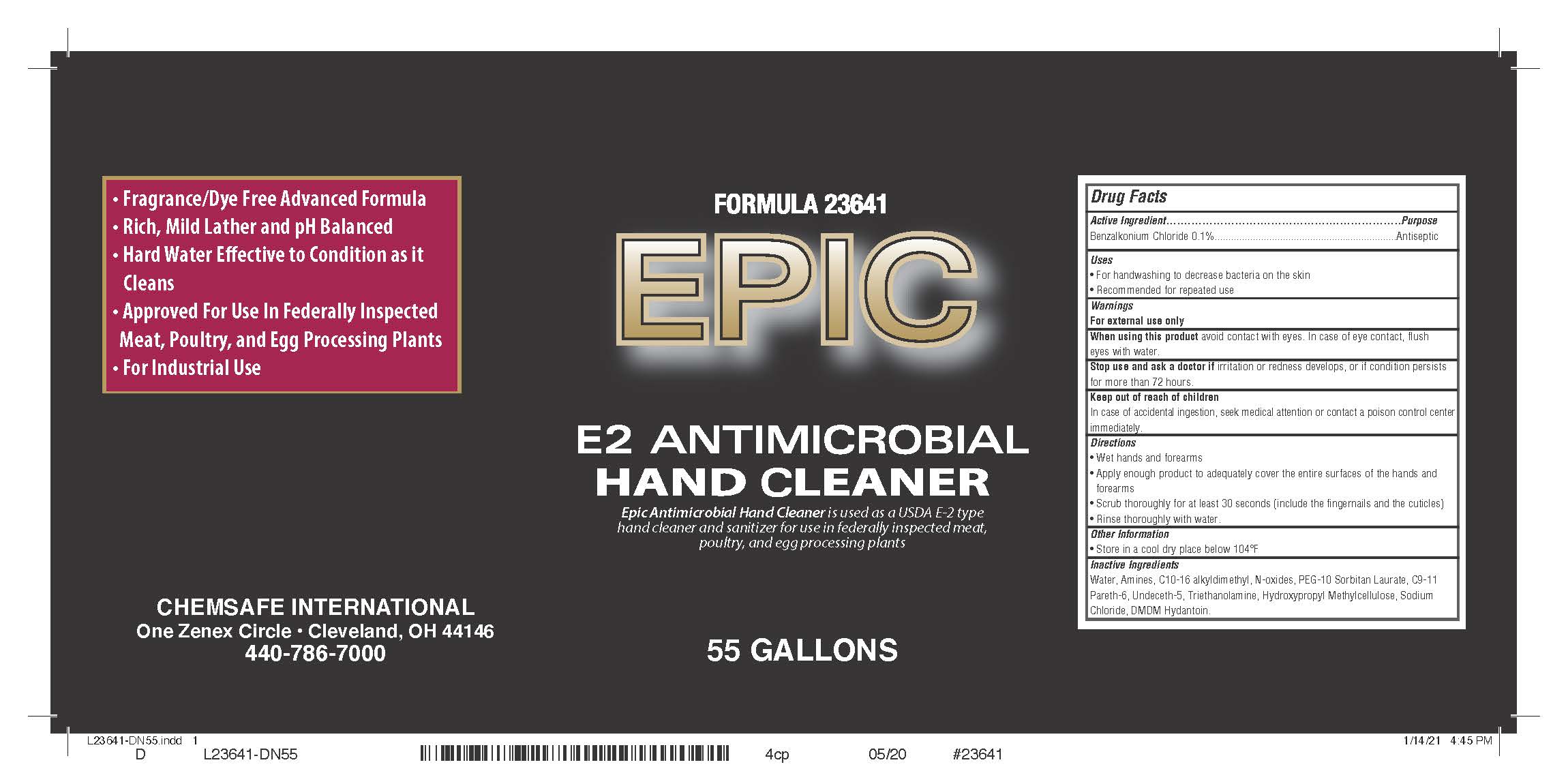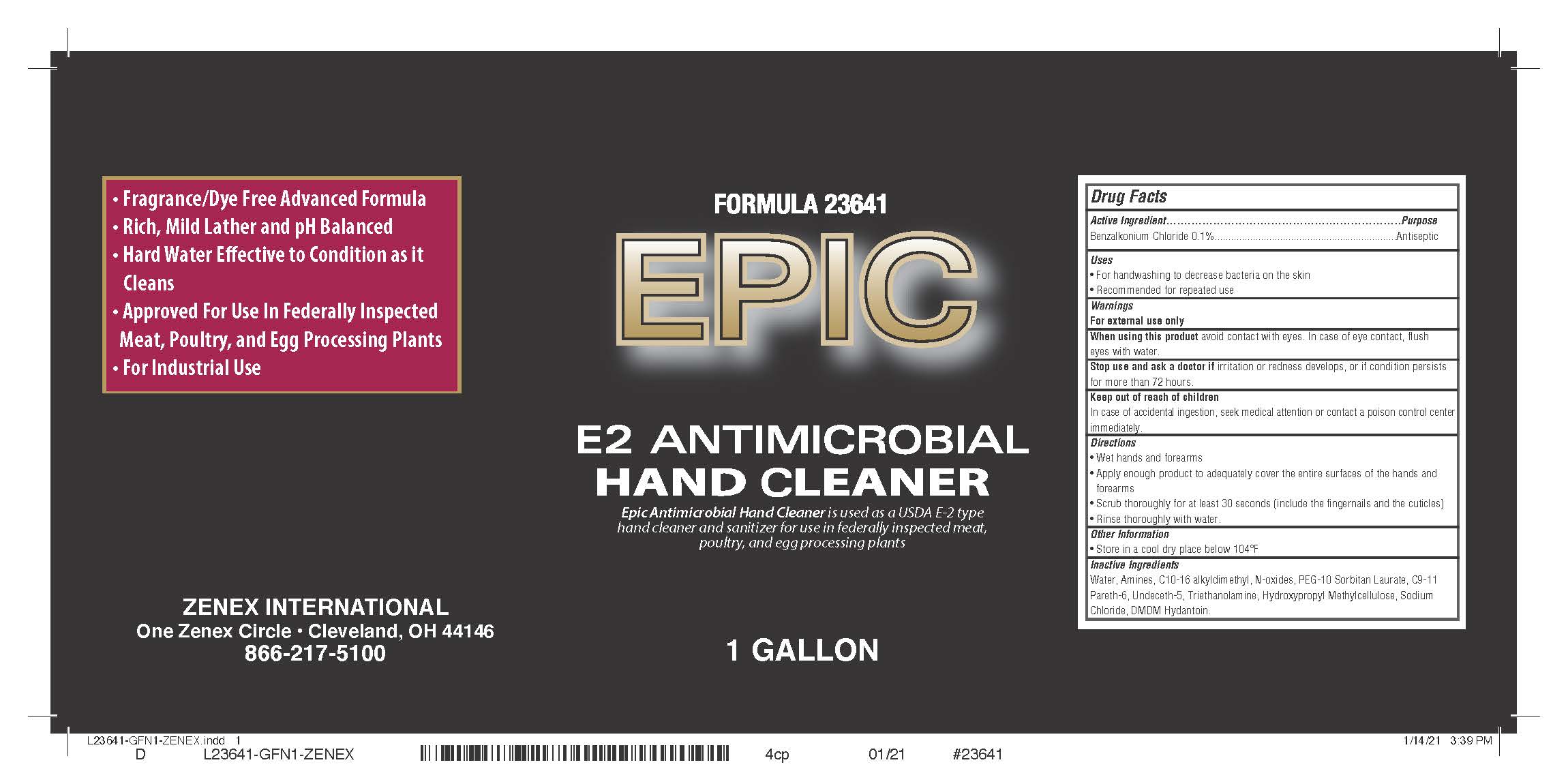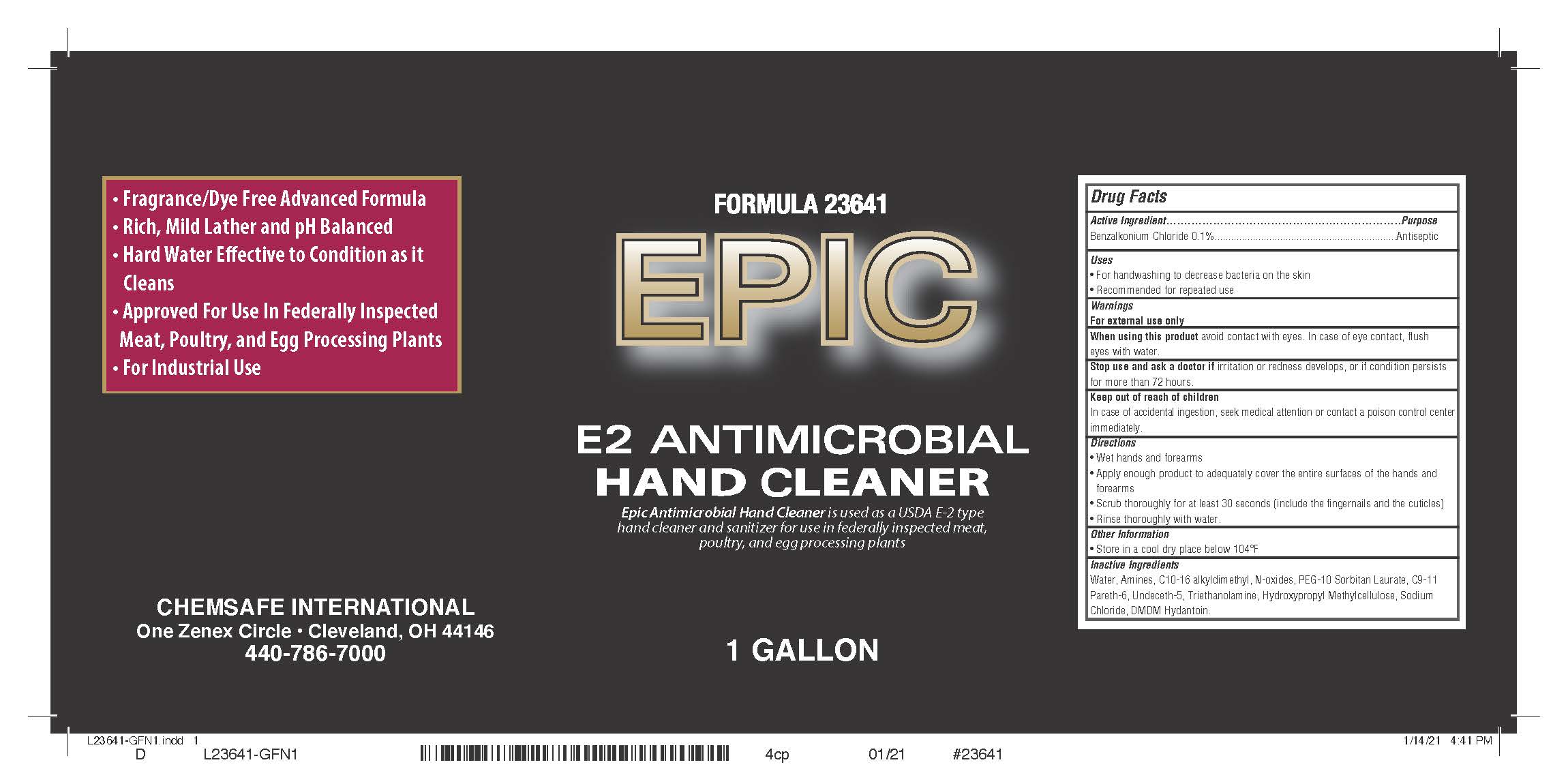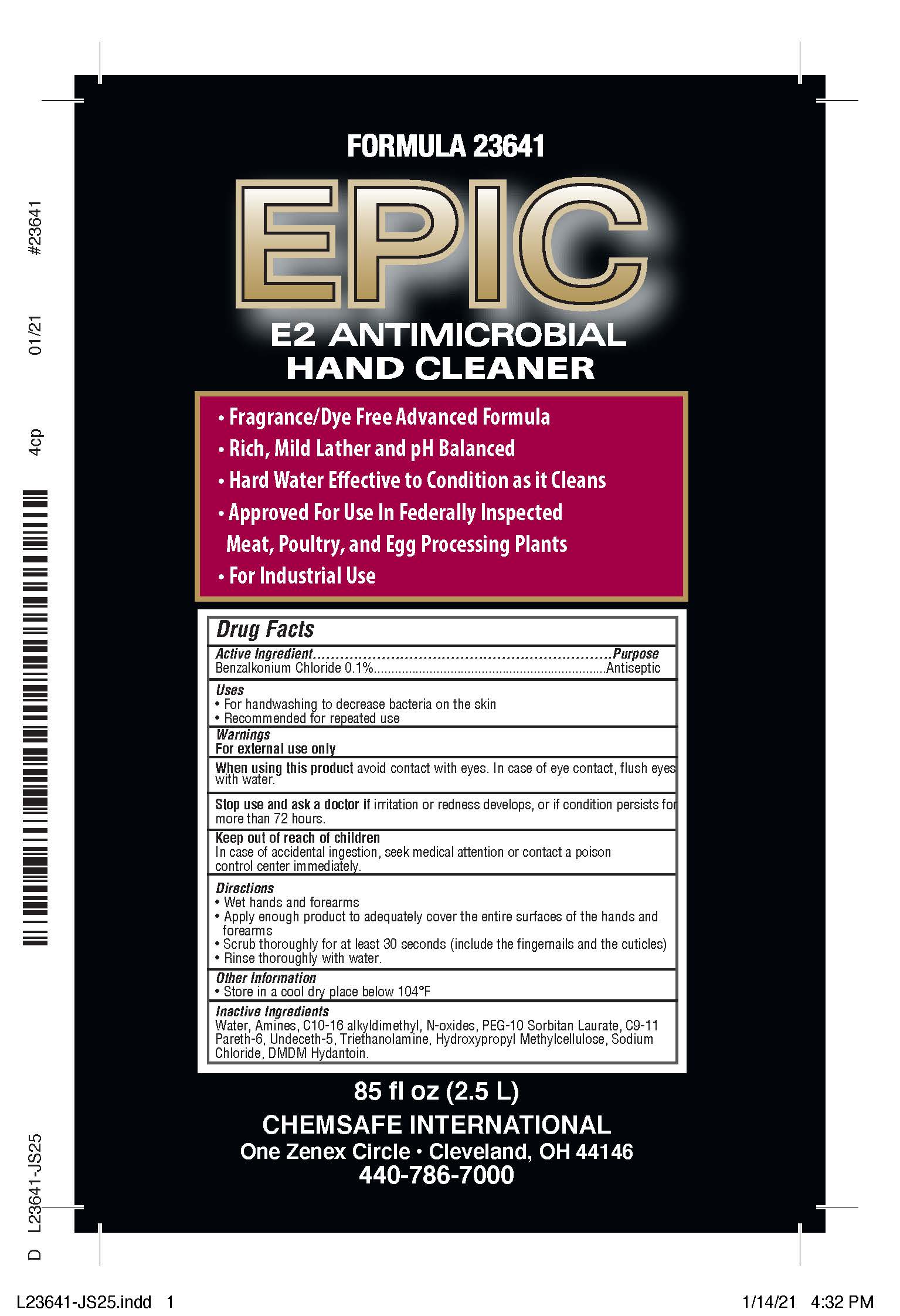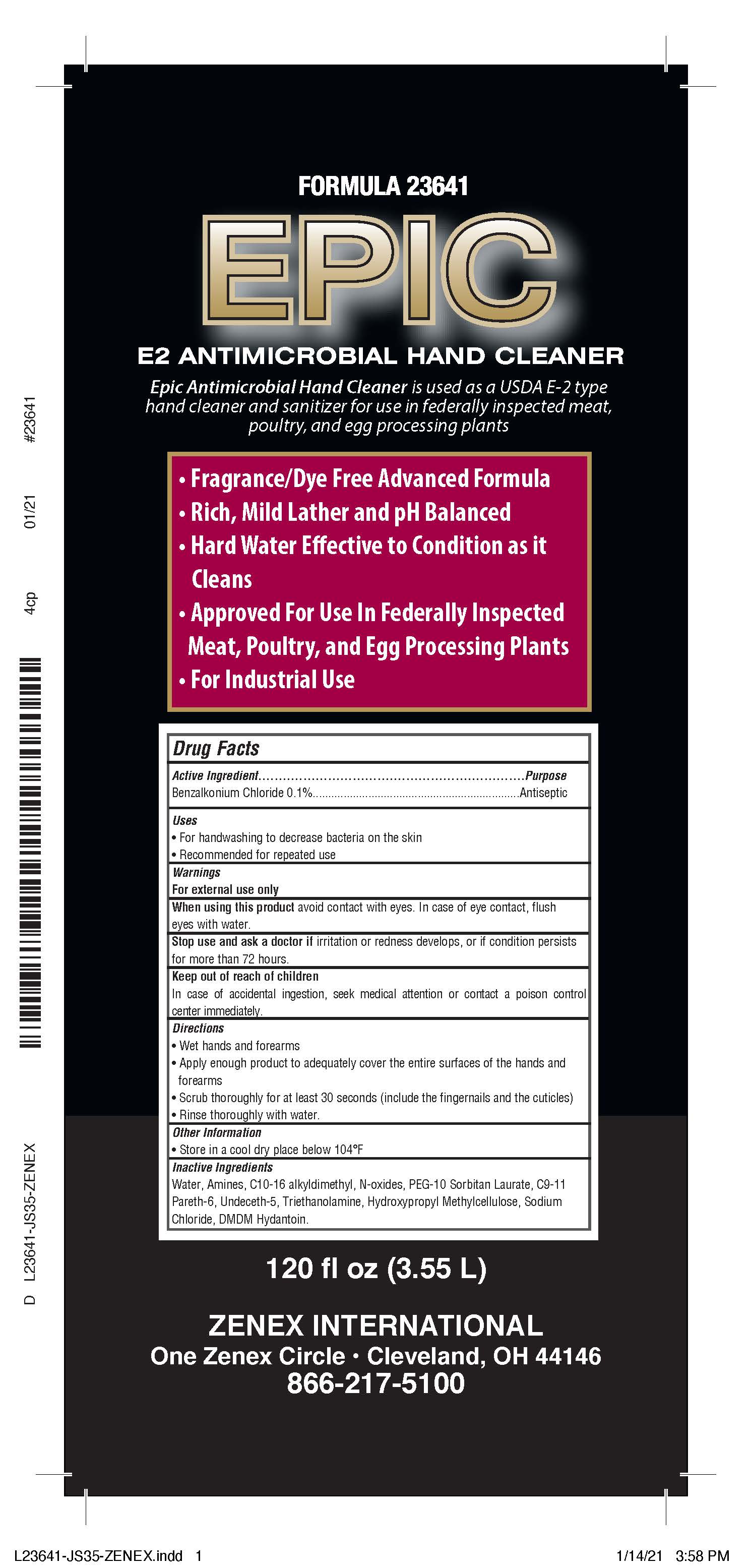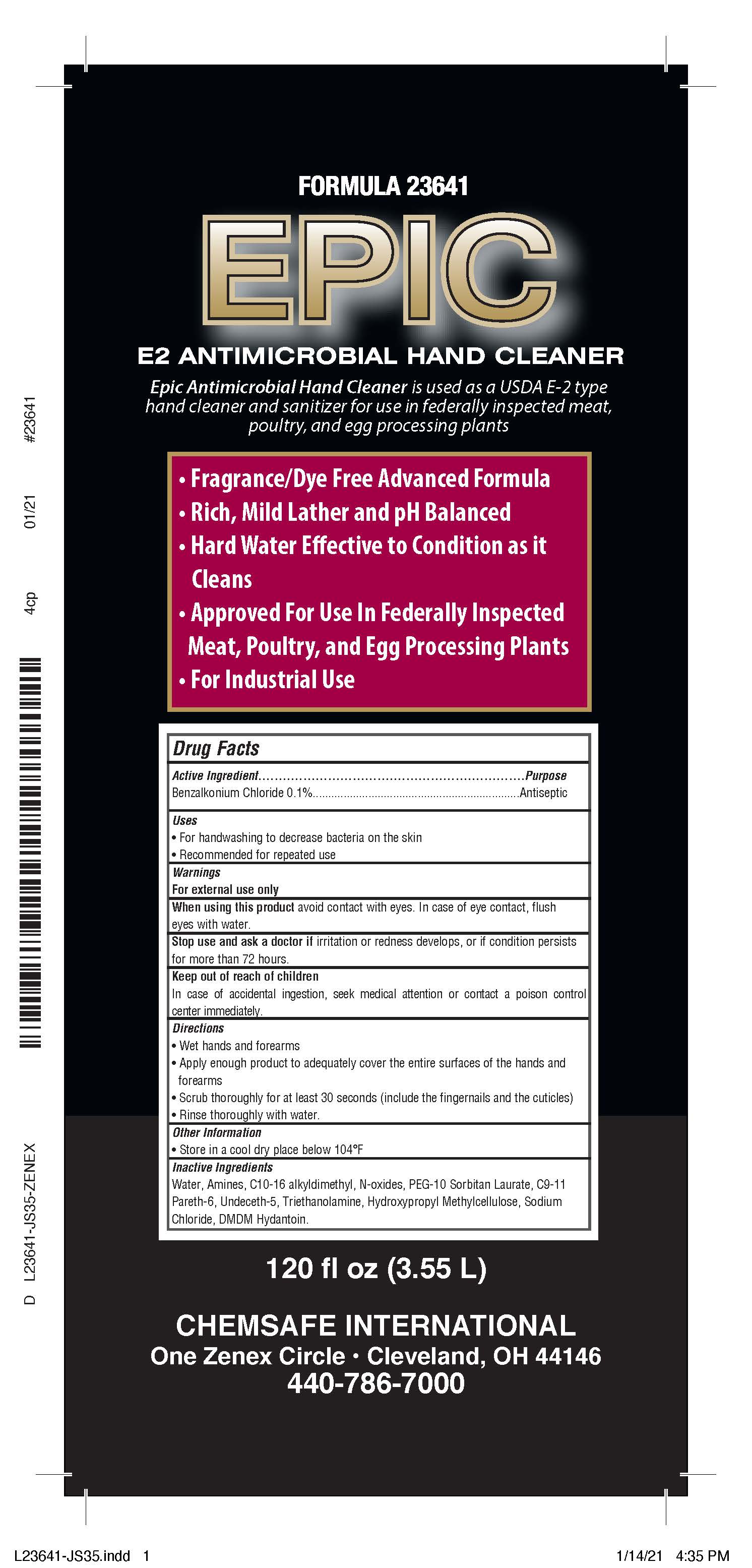 DRUG LABEL: Instant Foam
NDC: 74146-234 | Form: LIQUID
Manufacturer: GM Industrial, Inc.
Category: otc | Type: HUMAN OTC DRUG LABEL
Date: 20210127

ACTIVE INGREDIENTS: BENZALKONIUM CHLORIDE 1 mg/1 mL
INACTIVE INGREDIENTS: ACETAMIDOETHOXYETHANOL; CITRIC ACID MONOHYDRATE; COCAMIDOPROPYL PG-DIMONIUM CHLORIDE PHOSPHATE; DIHYDROXYETHYL COCAMINE OXIDE; WATER

236 Drug Facts Box

ACTIVE INGREDIENT

Benzalkonium Chloride 0.1%

PURPOSE

Antiseptic

Uses

- For handwashing to decrease bacteria on the skin
- Recommended for repeated use

WARNINGS

For external use only

When using this product avoid contact with eyes. In case of eye contact, flush eyes with water.

Stop use and ask a doctor if irritation or redness develops, or if condition persists for more than 72 hours.

Keep out of reach of children

In case of accidental ingestion, seek medical attention or contact a poison control center immediately.

Directions

- Wet hands and forearms
- Apply enough product to adequately cover the entire surfaces of the hands and forearms
- Scrub thoroughly for at least 30 seconds (include the fingernails and the cuticles)
- Rinse thoroughly with water.

Other Information

- Store in a cool dry place below 104°F

Inactive Ingredients

Water, Amines, C10-C16-alkyldimethyl, N,oxides, PEG-10 Sorbitan Laurate, C9-11 Pareth-6, Undeceth-5, Triethanolamine, Hydroxypropyl Methylcellulose, Sodium Chloride, DMDM Hydantoin.

234 Drug Facts Box

ACTIVE INGREDIENT

Benzalkonium Chloride 0.1%

PURPOSE

Antiseptic

Uses

- For hand sanitizing to decrease bacteria on the skin
- Recommended for repeated use

WARNINGS

For external use only. Do not use in eyes.

When using this product avoid contact with eyes. In case of eye contact, flush eyes with water.

Stop use and ask a doctor if irritation or redness develops, or if condition persists for more than 72 hours.

Keep out of reach of children. If swallowed, get medical help or contact a Poison Control Center right away.

Directions

- Pump a small amount of foam into palm of hand
- Rub thoroughly over all surfaces of both hands
- Rub hands together briskly until dry.

Inactive Ingredients

Water, Cocamidopropyl PG-dimonium chloride phosphate, Dihydroxyethyl cocamine oxide, Acetamidoethoxyethanol, Citric acid.

PACKAGE LABEL

1 GAL NDC: 74146-236-01

PACKAGE LABEL

1 GAL Box NDC: 74146-236-02 1 GAL Box NDC: 74146-236-02

PACKAGE LABEL

1 GAL NDC: 74146-236-03

PACKAGE LABEL

1 GAL Box NDC: 74146-236-04

PACKAGE LABEL

5 GAL NDC: 74146-236-05

PACKAGE LABEL

5 GAL NDC: 74146-236-06

PACKAGE LABEL

55 GAL NDC: 74146-236-07

PACKAGE LABEL

55 GAL NDC: 74146-236-08

PACKAGE LABEL

30 GAL NDC: 74146-236-09

PACKAGE LABEL

30 GAL NDC: 74146-236-10

PACKAGE LABEL

15 GAL NDC: 74146-236-11

PACKAGE LABEL

15 GAL NDC: 74146-236-12

PACKAGE LABEL

3.55 L Jug NDC: 74146-236-13

PACKAGE LABEL

3.55 L Jug Box NDC: 74146-236-14

PACKAGE LABEL

3.55 L Jug NDC: 74146-236-15

PACKAGE LABEL

3.55 L Jug Box NDC: 74146-236-16

PACKAGE LABEL

2.5 L NDC: 74146-236-17

PACKAGE LABEL

2.5 L Jug Box NDC: 74146-236-18

PACKAGE LABEL

2.5 L Jug NDC: 74146-236-19

PACKAGE LABEL

2.5 L Jug Box NDC: 74146-236-20

PACKAGE LABEL

1000 mL NDC: 74146-234-29

PACKAGE LABEL

1 gal NDC 74146-234-21

PACKAGE LABEL

5 gal NDC 74146-234-25

PACKAGE LABEL

55 gal NDC 74146-234-27

PACKAGE LABEL

1000 mL NDC 74146-234-30

PACKAGE LABEL

1 Gal NDC 74146-234-22

PACKAGE LABEL

1000 mL NDC 74146-234-31

PACKAGE LABEL

5 Gal NDC 74146-234-26

PACKAGE LABEL

55 Gal NDC 74146-234-28

PACKAGE LABEL

1 gal NDC 74146-234-23

PACKAGE LABEL

1000 mL NDC 74146-234-32

PACKAGE LABEL

1 Gal NDC 74146-234-24